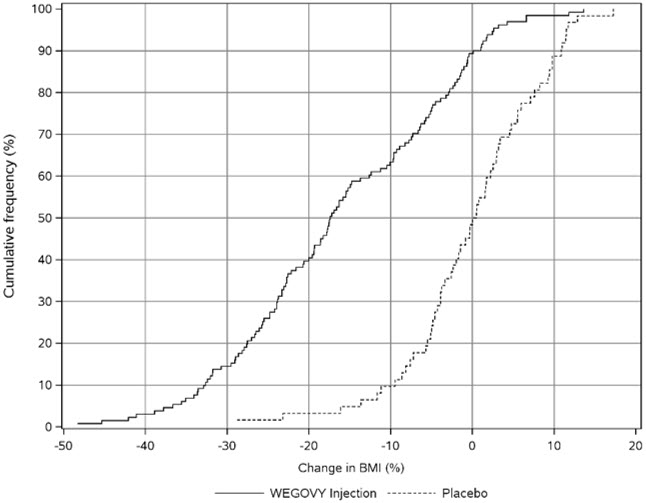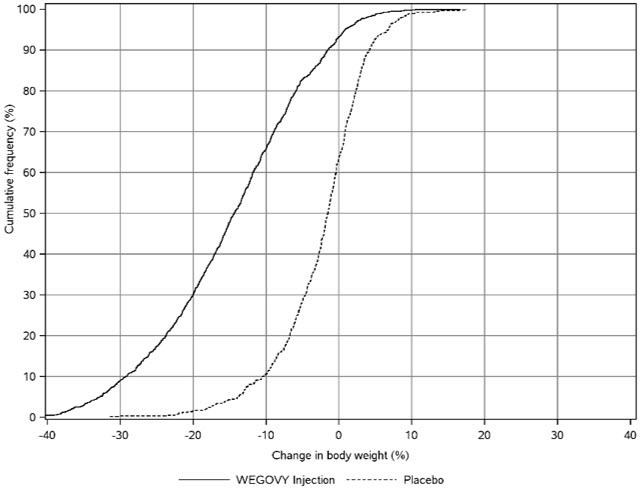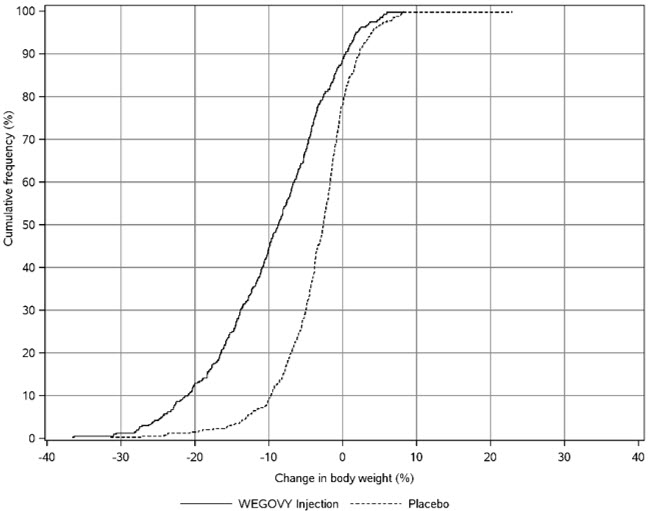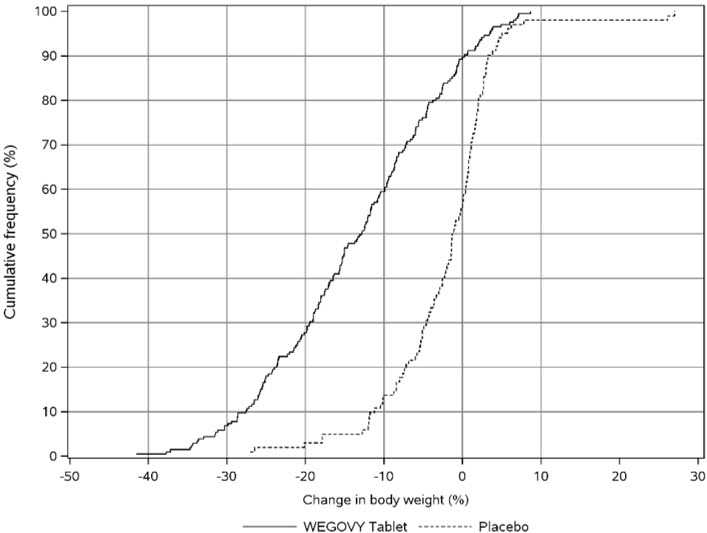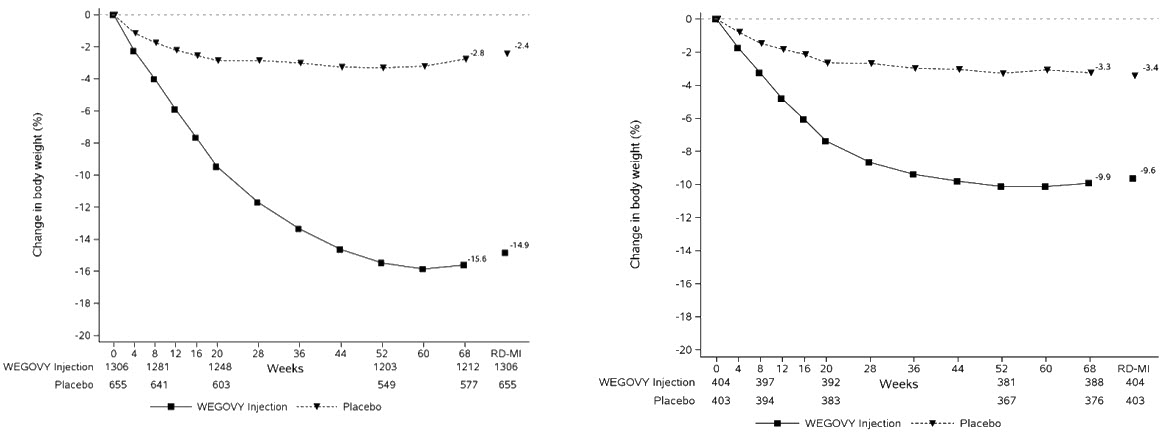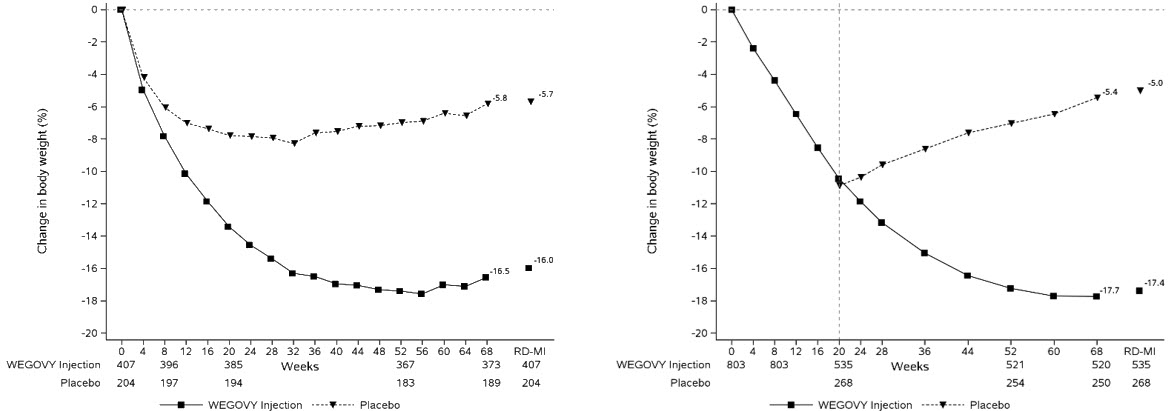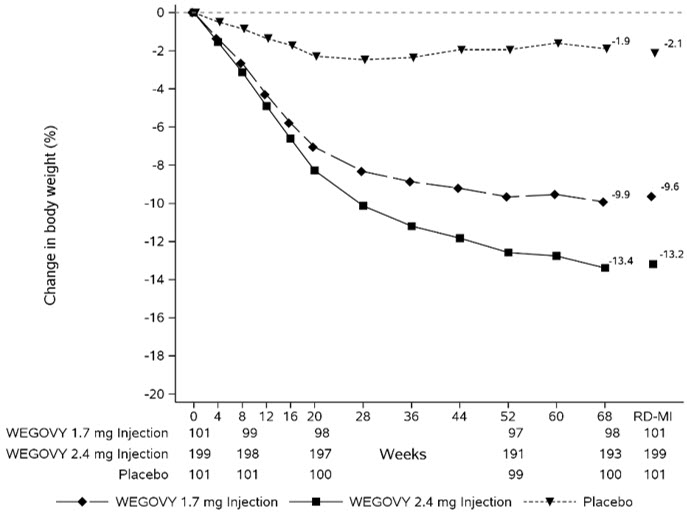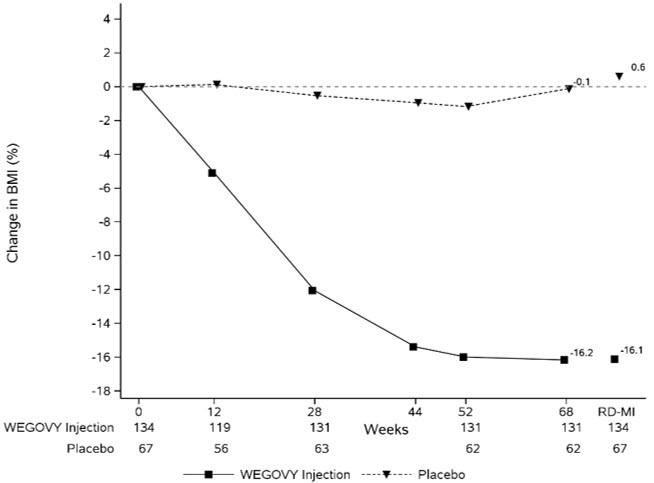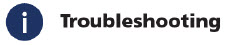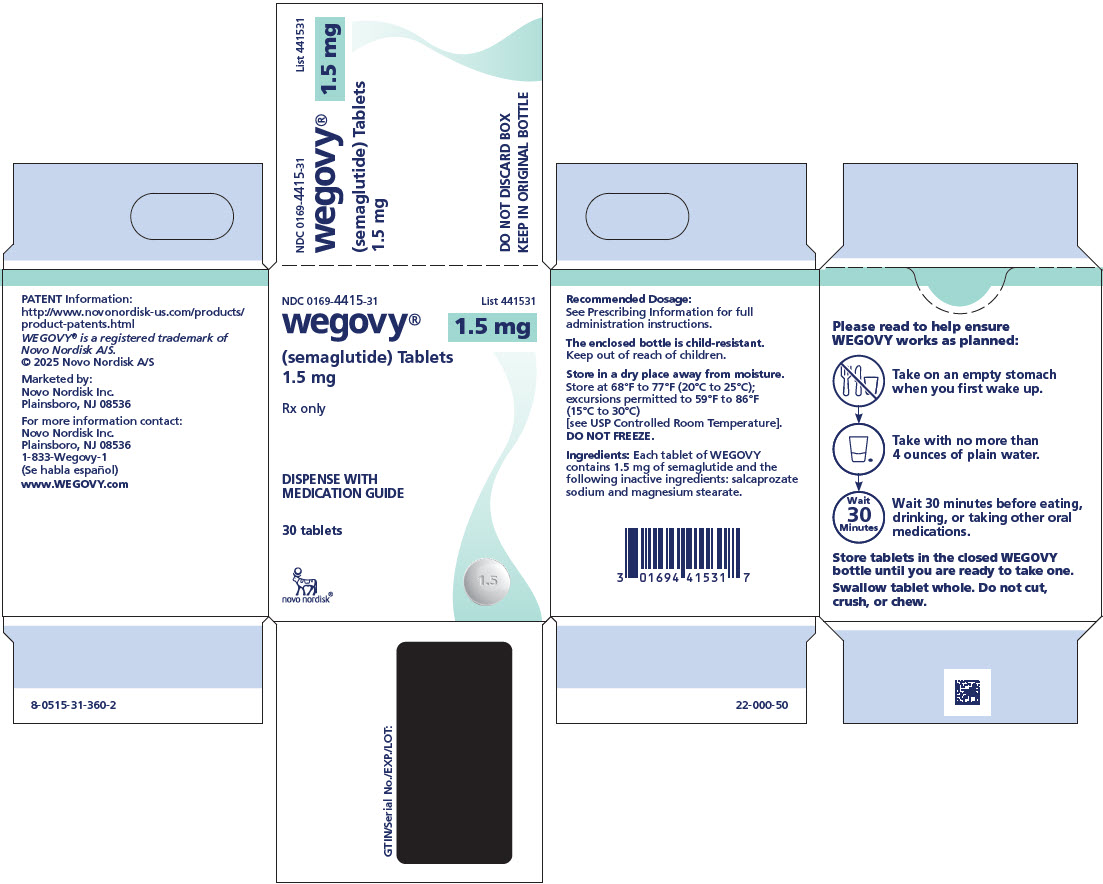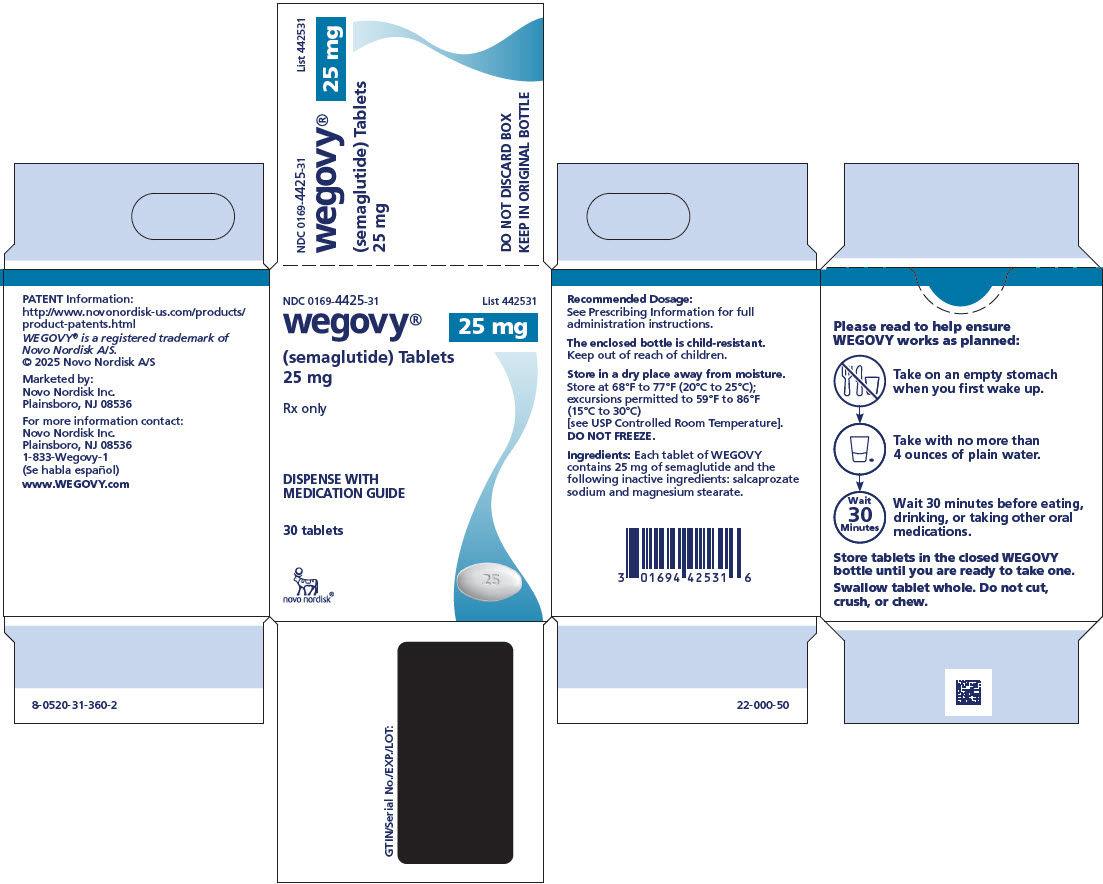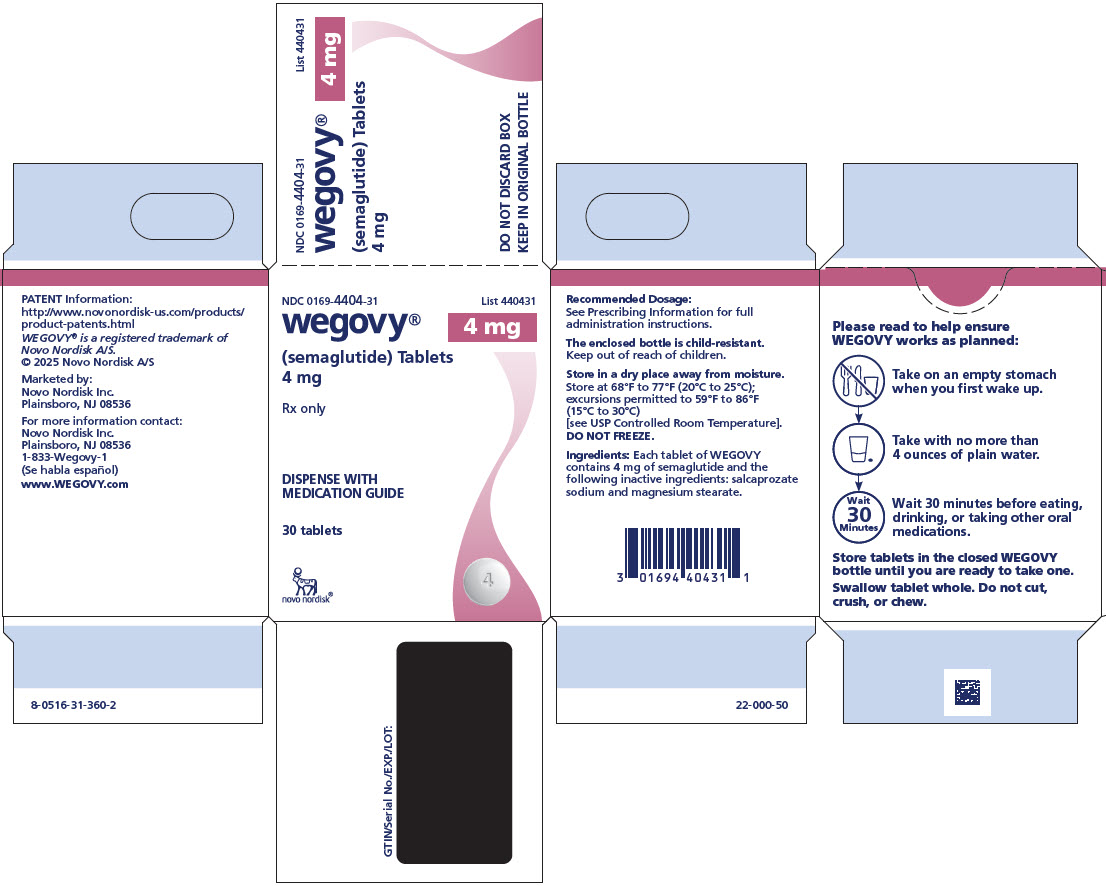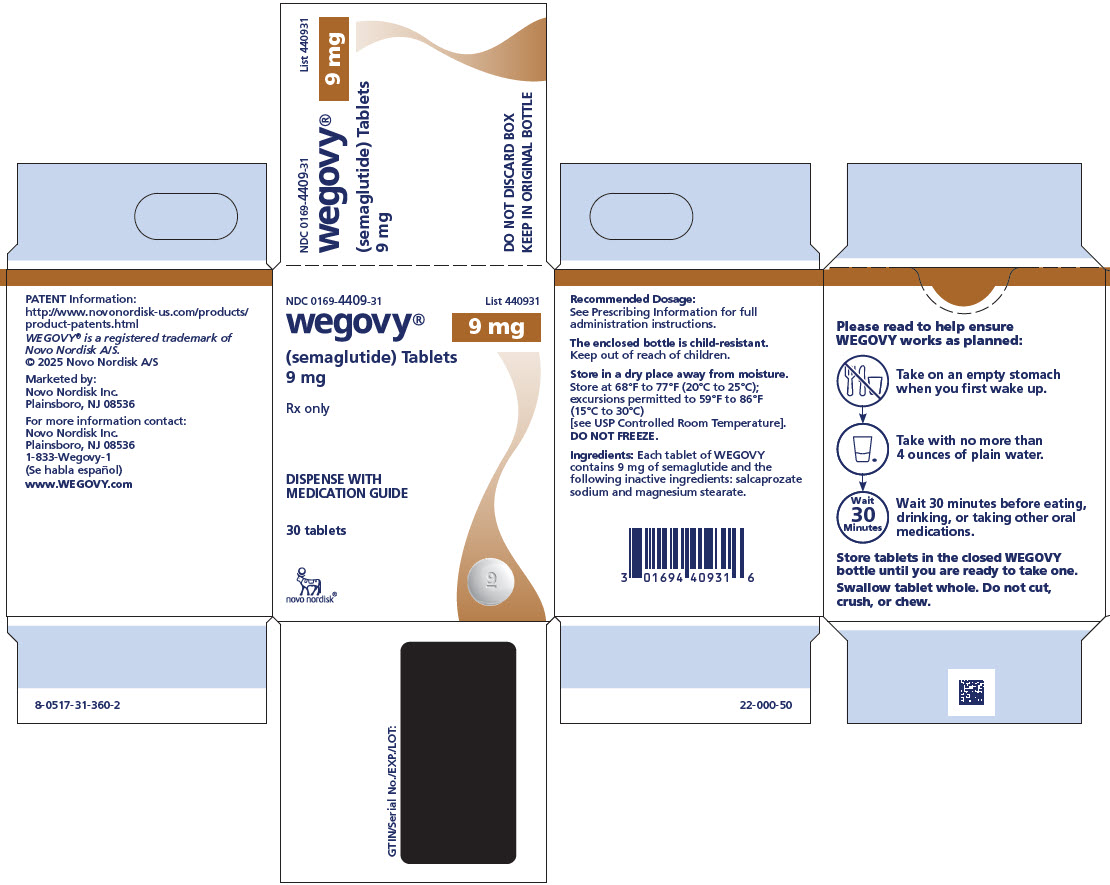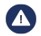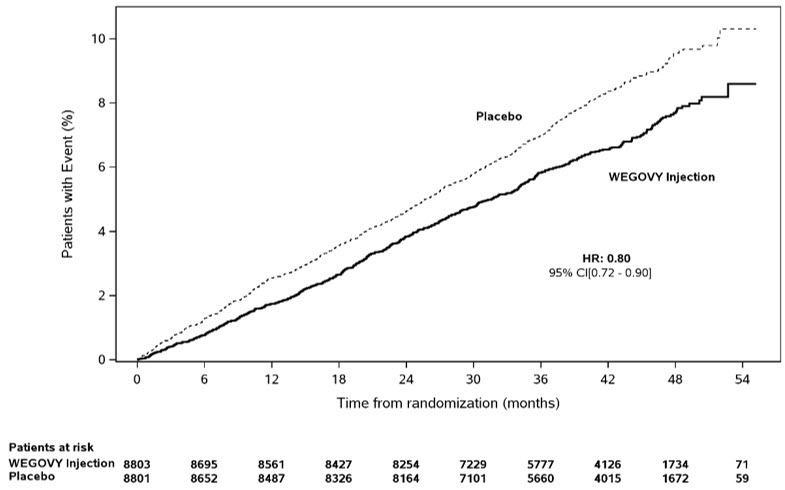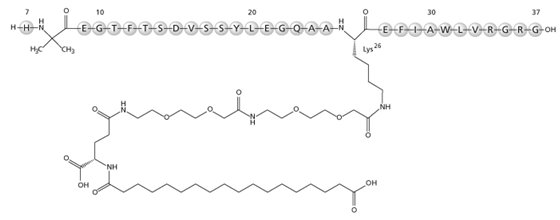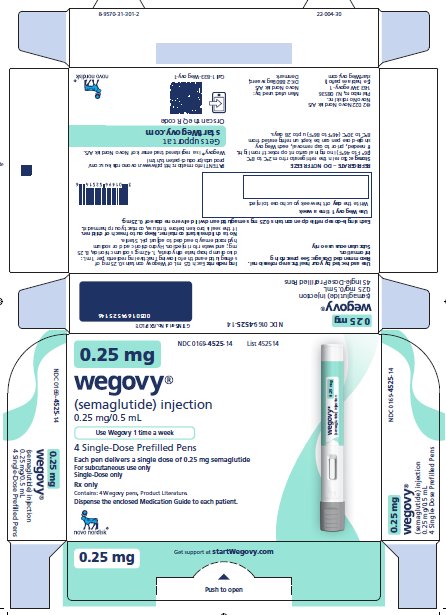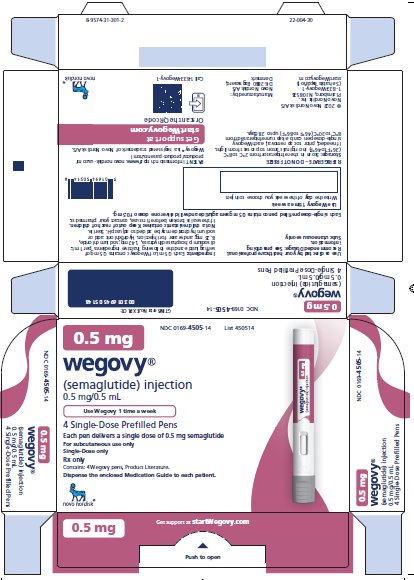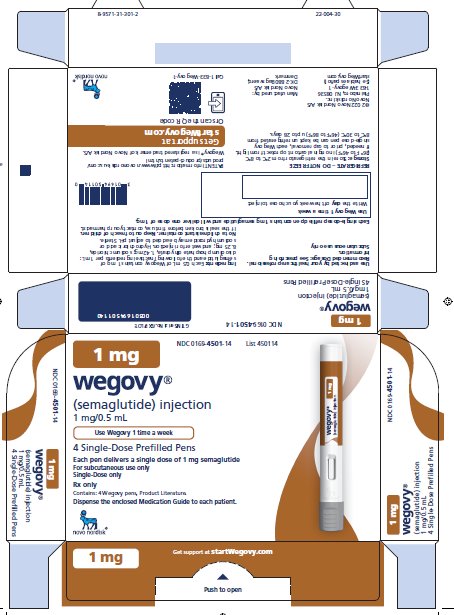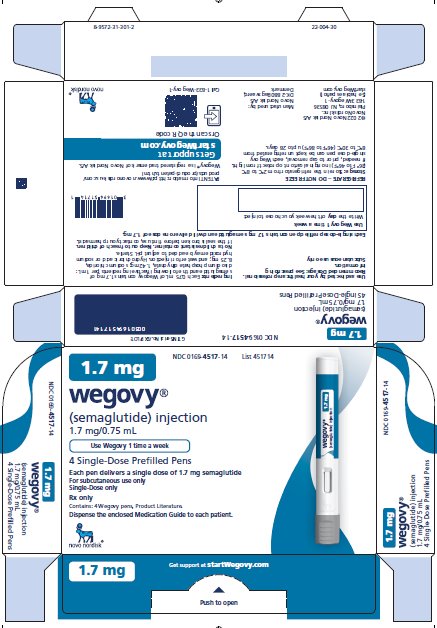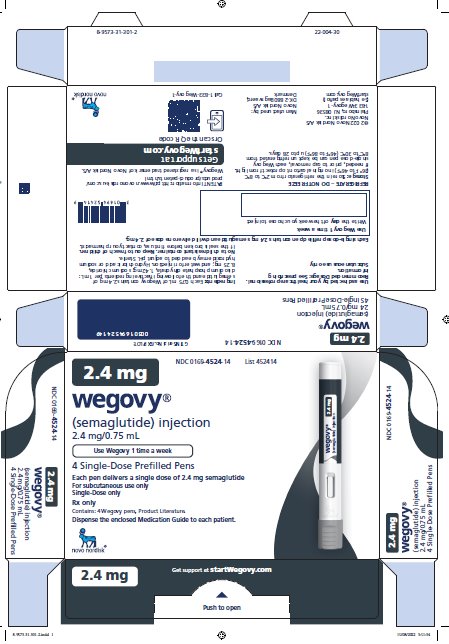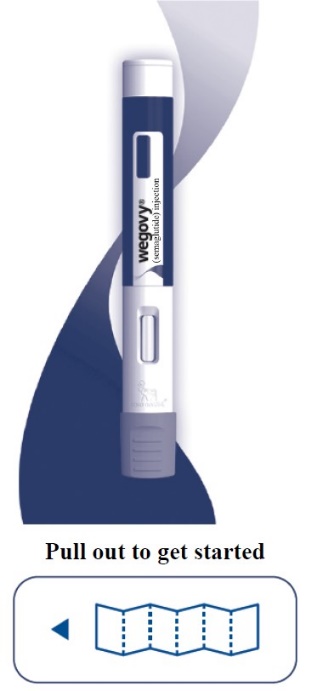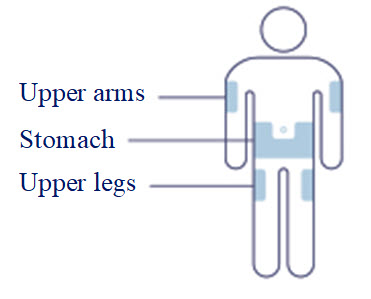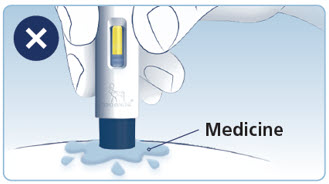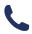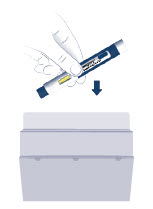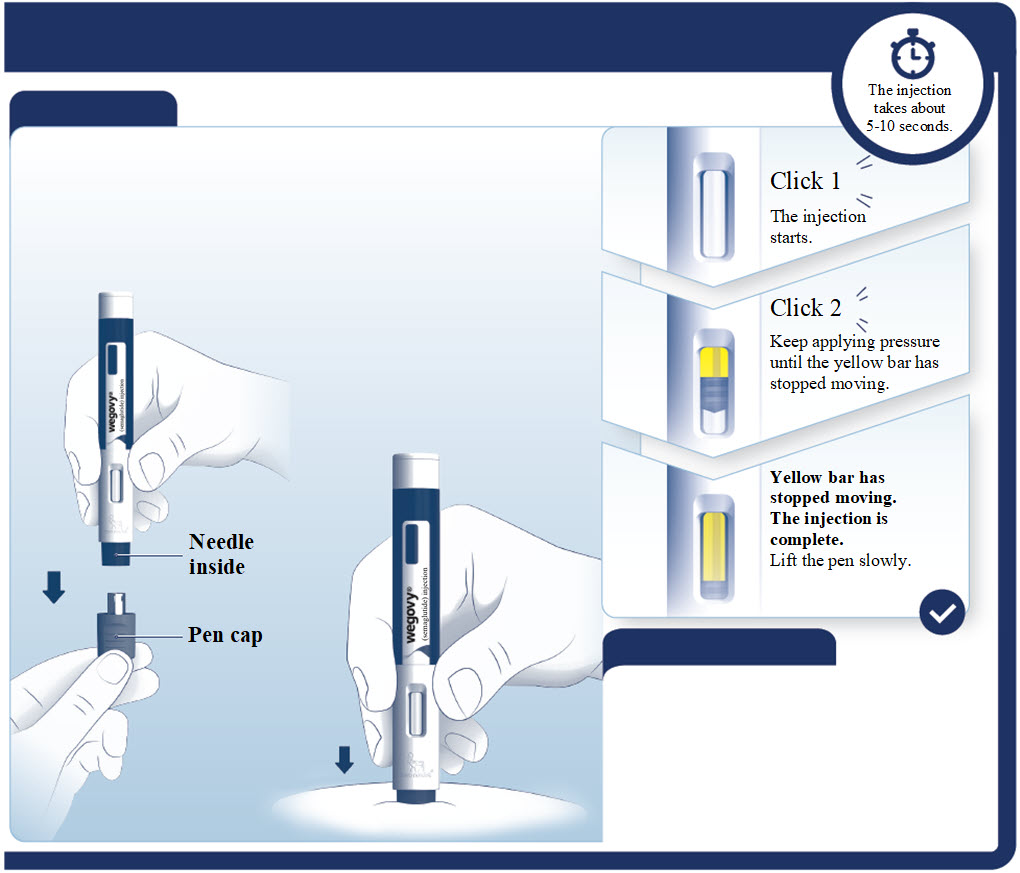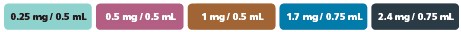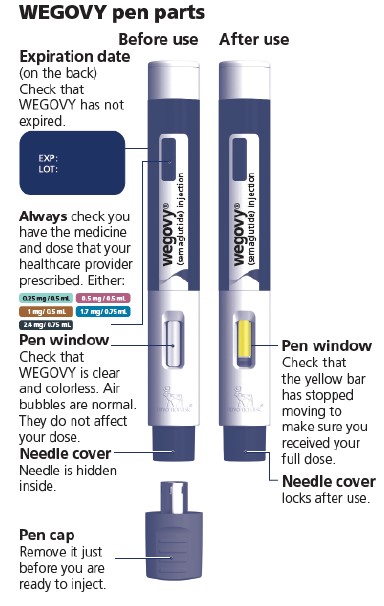 DRUG LABEL: WEGOVY
NDC: 0169-4525 | Form: INJECTION, SOLUTION
Manufacturer: Novo Nordisk
Category: prescription | Type: HUMAN PRESCRIPTION DRUG LABEL
Date: 20260130

ACTIVE INGREDIENTS: SEMAGLUTIDE 0.25 mg/0.5 mL
INACTIVE INGREDIENTS: SODIUM PHOSPHATE, DIBASIC, DIHYDRATE; SODIUM CHLORIDE; WATER

HIGHLIGHTS OF PRESCRIBING INFORMATION

These highlights do not include all the information needed to use WEGOVY® safely and effectively. See full prescribing information for WEGOVY.
WEGOVY (semaglutide) injection, for subcutaneous use
WEGOVY (semaglutide) tablets, for oral use
Initial U.S. Approval: 2017

RECENT MAJOR CHANGES

Indications and Usage (1) …..………………………………08/2025, 12/2025

Dosage and Administration (2)……………..……………….08/2025, 12/2025

Warnings and Precautions,

Acute Kidney Injury Due to Volume Depletion (5.5)..………….08/2025
Severe Gastrointestinal Adverse Reactions (5.6)………………..10/2025

WARNING: RISK OF THYROID C-CELL TUMORS

See full prescribing information for complete boxed warning.

- In rodents, semaglutide causes thyroid C-cell tumors at clinically relevant exposures. It is unknown whether WEGOVY causes thyroid C-cell tumors, including medullary thyroid carcinoma (MTC), in humans as the human relevance of semaglutide-induced rodent thyroid C-cell tumors has not been determined. (5.1, 13.1)
- WEGOVY is contraindicated in patients with a personal or family history of MTC or in patients with Multiple Endocrine Neoplasia syndrome type 2 (MEN 2). Counsel patients regarding the potential risk of MTC and symptoms of thyroid tumors. (4, 5.1)

1 INDICATIONS AND USAGE

WEGOVY is a glucagon-like peptide-1 (GLP-1) receptor agonist.

WEGOVY injection is indicated in combination with a reduced calorie diet and increased physical activity:

- to reduce the risk of major adverse cardiovascular (CV) events (CV death, non-fatal myocardial infarction, or non-fatal stroke) in adults with established CV disease and either obesity or overweight. (1)
- to reduce excess body weight and maintain weight reduction long term in:
- Adults and pediatric patients aged 12 years and older with obesity. (1)
- Adults with overweight in the presence of at least one weight-related comorbid condition. (1)
- for the treatment of noncirrhotic metabolic dysfunction-associated steatohepatitis (MASH), formerly known as nonalcoholic steatohepatitis (NASH), with moderate to advanced liver fibrosis (consistent with stages F2 to F3 fibrosis) in adults. This indication is approved under accelerated approval based on improvement of MASH and fibrosis [see Clinical Studies (14.4)]. Continued approval for this indication may be contingent upon the verification and description of clinical benefit in a confirmatory trial. (1)

WEGOVY tablets are indicated in combination with a reduced calorie diet and increased physical activity:

• To reduce the risk of major adverse CV events (CV death, non-fatal myocardial infarction, or non-fatal stroke) in adults with established CV disease and either obesity or overweight. (1)
• To reduce excess body weight and maintain weight reduction long term in adults with obesity, or in adults with overweight in the presence of at least one weight-related comorbid condition. (1)

Limitations of Use:

• Concomitant use of WEGOVY (semaglutide) tablets or WEGOVY (semaglutide) injection with other semaglutide-containing products or with any other GLP-1 receptor agonist is not recommended. (1)

2 DOSAGE AND ADMINISTRATION

In patients with diabetes, monitor blood glucose prior to starting and during WEGOVY treatment. (2.1)

WEGOVY Injection

- Administer WEGOVY injection once weekly as an adjunct to diet and increased physical activity, on the same day each week, at any time of day, with or without meals. (2.1)
- Inject subcutaneously in the abdomen, thigh, or upper arm. (2.1)
- Initiate at 0.25 mg once weekly for 4 weeks. Then follow the dosage escalation schedule in Table 1, titrating every 4 weeks to achieve the maintenance dosage. (2.2)
- The usual recommended maintenance dosage of WEGOVY injection is 2.4 mg once weekly. Refer to the full PI for maintenance dosages based on the indication. (2.2)

WEGOVY Tablets

- Take WEGOVY tablets orally once-daily on an empty stomach in the morning with water (up to 4 ounces). Do not take with other liquids besides water (2.1).
- Swallow tablets whole. Do not split, crush, chew or dissolve. (2.1)
- After taking WEGOVY tablet wait at least 30 minutes before eating food, drinking beverages or taking other oral medications. (2.1)
- Initiate WEGOVY tablet with a dosage of 1.5 mg once daily for 30 days. Then follow the dosage escalation schedule, titrating every 30 days to achieve the maintenance dosage. (2.2)
- The recommended maintenance dosage of WEGOVY tablets is 25 mg orally once daily for cardiovascular risk reduction and weight reduction in adults

3 DOSAGE FORMS AND STRENGTHS

- Injection: prefilled, single-dose pen that delivers doses of 0.25 mg, 0.5 mg, 1 mg, 1.7 mg or 2.4 mg (3)
- Tablets: 1.5 mg, 4 mg, 9 mg and 25 mg (3)

4 CONTRAINDICATIONS

- Personal or family history of MTC or in patients with MEN 2. (4)
- Known hypersensitivity to semaglutide or any of the excipients in WEGOVY tablets or WEGOVY injection. (4)

5 WARNINGS AND PRECAUTIONS

- Acute Pancreatitis: Has been observed in patients treated with GLP-1 receptor agonists, including WEGOVY. Discontinue if pancreatitis is suspected. (5.2)
- Acute Gallbladder Disease: Has occurred in clinical trials. If cholelithiasis is suspected, gallbladder studies and clinical follow-up are indicated. (5.3)
- Hypoglycemia: Concomitant use with insulin or an insulin secretagogue may increase the risk of hypoglycemia, including severe hypoglycemia. Reducing the dose of insulin or insulin secretagogue may be necessary. Inform all patients of the risk of hypoglycemia and educate them on the signs and symptoms of hypoglycemia. (5.4)
- Acute Kidney Injury Due to Volume Depletion: Monitor renal function in patients reporting adverse reactions that could lead to volume depletion. (5.5)
- Severe Gastrointestinal Adverse Reactions: Use has been associated with gastrointestinal adverse reactions, sometimes severe. WEGOVY is not recommended in patients with severe gastroparesis. (5.6)
- Hypersensitivity Reactions: Anaphylactic reactions and angioedema have been reported postmarketing. Discontinue WEGOVY if suspected and promptly seek medical advice. (5.7)
- Diabetic Retinopathy Complications in Patients with Type 2 Diabetes: Has been reported in trials with semaglutide. Patients with a history of diabetic retinopathy should be monitored. (5.8)
- Heart Rate Increase: Monitor heart rate at regular intervals. (5.9)
- Suicidal Behavior and Ideation: Monitor for depression or suicidal thoughts. Discontinue WEGOVY if symptoms develop. (5.10)
- Pulmonary Aspiration During General Anesthesia or Deep Sedation: Has been reported in patients receiving GLP-1 receptor agonists undergoing elective surgeries or procedures. Instruct patients to inform healthcare providers of any planned surgeries or procedures. (5.11)

6 ADVERSE REACTIONS

Most common adverse reactions (incidence ≥5%) in adults or pediatric patients aged 12 years and older are: nausea, diarrhea, vomiting, constipation, abdominal pain, headache, fatigue, dyspepsia, dizziness, abdominal distension, eructation, hypoglycemia in patients with type 2 diabetes, flatulence, gastroenteritis, gastroesophageal reflux disease, and nasopharyngitis. (6.1)

To report SUSPECTED ADVERSE REACTIONS, contact Novo Nordisk Inc., at 1-833-934-6891 or FDA at 1-800-FDA-1088 or www.fda.gov/medwatch.

7 DRUG INTERACTIONS

WEGOVY delays gastric emptying. May impact absorption of concomitantly administered oral medications. Consider increased clinical or laboratory monitoring when used concomitantly with other oral medications that have a narrow therapeutic index or that require clinical monitoring. (7.2)

8 USE IN SPECIFIC POPULATIONS

- Pregnancy: May cause fetal harm. For patients receiving WEGOVY for CV risk reduction or weight reduction, discontinue WEGOVY when pregnancy is recognized. For patients with MASH, use during pregnancy only if the potential benefit justifies the potential risk to the fetus. (8.1)
- Lactation: Breastfeeding not recommended during treatment with WEGOVY tablets. (8.2)
- Females and Males of Reproductive Potential: For patients receiving WEGOVY for CV risk reduction or weight reduction, or for MASH where the potential risk outweighs the potential benefit, discontinue WEGOVY at least 2 months before a planned pregnancy because of the long half-life of semaglutide. (8.3)

FULL PRESCRIBING INFORMATION

WARNING: RISK OF THYROID C-CELL TUMORS

- In rodents, semaglutide causes dose-dependent and treatment-duration-dependent thyroid C-cell tumors at clinically relevant exposures. It is unknown whether WEGOVY causes thyroid C-cell tumors, including medullary thyroid carcinoma (MTC), in humans as human relevance of semaglutide-induced rodent thyroid C-cell tumors has not been determined [see Warnings and Precautions (5.1), Nonclinical Toxicology (13.1)].
- WEGOVY is contraindicated in patients with a personal or family history of MTC or in patients with Multiple Endocrine Neoplasia syndrome type 2 (MEN 2) [see Contraindications (4)]. Counsel patients regarding the potential risk for MTC with the use of WEGOVY and inform them of symptoms of thyroid tumors (e.g., a mass in the neck, dysphagia, dyspnea, persistent hoarseness). Routine monitoring of serum calcitonin or using thyroid ultrasound is of uncertain value for early detection of MTC in patients treated with WEGOVY [see Contraindications (4), Warnings and Precautions (5.1)].

1 INDICATIONS AND USAGE

WEGOVY injection is indicated in combination with a reduced calorie diet and increased physical activity:

- To reduce the risk of major adverse cardiovascular (CV) events (CV death, non-fatal myocardial infarction, or non-fatal stroke) in adults with established CV disease and either obesity or overweight.
- To reduce excess body weight and maintain weight reduction long term in:
  - Adults and pediatric patients aged 12 years and older with obesity.
  - Adults with overweight in the presence of at least one weight-related comorbid condition.
- For the treatment of noncirrhotic metabolic dysfunction-associated steatohepatitis (MASH), formerly known as nonalcoholic steatohepatitis (NASH), with moderate to advanced liver fibrosis (consistent with stages F2 to F3 fibrosis) in adults. This indication is approved under accelerated approval based on improvement of MASH and fibrosis [see Clinical Studies (14.4)]. Continued approval for this indication may be contingent upon the verification and description of clinical benefit in a confirmatory trial.

WEGOVY tablets are indicated in combination with a reduced calorie diet and increased physical activity:

- To reduce the risk of major adverse CV events (CV death, non-fatal myocardial infarction, or non-fatal stroke) in adults with established CV disease and either obesity or overweight.
- To reduce excess body weight and maintain weight reduction long term in adults with obesity, or in adults with overweight in the presence of at least one weight-related comorbid condition.

Limitations of Use

Concomitant use of WEGOVY (semaglutide) tablets or WEGOVY (semaglutide) injection with other semaglutide-containing products or with any other GLP-1 receptor agonist is not recommended.

2 DOSAGE AND ADMINISTRATION

2.1 Important Monitoring and Administration Instructions

In patients with diabetes mellitus, monitor blood glucose prior to starting WEGOVY and during WEGOVY treatment [see Warnings and Precautions (5.4)].

Administer WEGOVY in combination with a reduced-calorie diet and increased physical activity.

WEGOVY Injection

- Prior to initiation of WEGOVY injection, train patients on proper injection technique. Refer to the accompanying Instructions for Use for complete administration instructions with illustrations.
- Visually inspect the WEGOVY injection prior to each administration. Only use if solution is clear, colorless, and contains no particles.
- Administer WEGOVY injection once weekly, on the same day each week, at any time of day, with or without meals.
- Inject WEGOVY subcutaneously in the abdomen, thigh, or upper arm. The time of day and the injection site can be changed without the need for a dosage modification.

WEGOVY Tablets

- Take one WEGOVY tablet orally once daily on an empty stomach in the morning with water (up to 4 ounces). Do not take WEGOVY tablets with other liquids besides water [see Clinical Pharmacology (12.3)].
- Do not take more than one tablet per day.
- Swallow tablets whole. Do not split, crush, chew or dissolve in any solution.
- After taking a WEGOVY tablet, wait at least 30 minutes before eating food, drinking beverages or taking other oral medications [see Clinical Pharmacology (12.3)].

2.2 Recommended Dosage for WEGOVY Injection

Recommended Starting Dosage and Dosage Escalation of WEGOVY Injection for All Approved Indications

- The recommended starting dosage of WEGOVY injection is 0.25 mg administered subcutaneously once weekly.
- Follow the dosage escalation in Table 1 to reduce the risk of gastrointestinal adverse reactions [see Warnings and Precautions (5.6), Adverse Reactions (6.1)].
- If patients do not tolerate a dose during dosage escalation, consider delaying dosage escalation for 4 weeks.

Table 1. Recommended Starting Dosage and Dosage Escalation of WEGOVY Injection for All Approved Indications in Adults and Pediatric Patients Aged 12 Years and Older

 | Weeks | Once-weekly Subcutaneous Injection Dosage
Starting Dosage | 1 through 4 | 0.25 mg
Dosage Escalation | 5 through 8 | 0.5 mg
Dosage Escalation | 9 through 12 | 1 mg
Dosage Escalation | 13 through 16 | 1.7 mg
Maintenance Dosage | 17 and onward | See the indication below for the recommended maintenance dosage(s)

Recommended Maintenance Dosage of WEGOVY Injection for Approved Indications

Cardiovascular Risk Reduction in Adults

- The maintenance dosage of WEGOVY injection for cardiovascular risk reduction in adults is either 2.4 mg (recommended) or 1.7 mg once weekly.
- Consider treatment response and tolerability when selecting the maintenance dosage [see Adverse Reactions (6.1), Clinical Studies (14.1)].

Weight Reduction in Adults and Pediatric Patients Aged 12 Years and Older

The maintenance dosage of WEGOVY injection for weight reduction in adults and pediatric patients aged 12 years and older is either 2.4 mg (recommended) or 1.7 mg once weekly.

Consider treatment response and tolerability when selecting the maintenance dosage [see Adverse Reactions (6.1), Clinical Studies (14.2, 14.3)].

Noncirrhotic MASH with Moderate to Advanced Liver Fibrosis in Adults

The recommended maintenance dosage of WEGOVY injection for the treatment of noncirrhotic MASH with moderate to advanced liver fibrosis in adults is 2.4 mg injected subcutaneously once weekly. If patients do not tolerate the maintenance dosage of 2.4 mg once weekly, the dosage can be decreased to 1.7 mg once weekly. Consider reescalation to 2.4 mg once weekly [see Adverse Reactions (6.1), Clinical Studies (14.4)].

2.3 Recommended Dosage of WEGOVY Tablets

Recommended Dosage of WEGOVY Tablets for Cardiovascular Risk Reduction or Weight Reduction in Adults

- The recommended starting dosage of WEGOVY tablets is 1.5 mg taken orally once daily. Follow the dosage escalation in Table 2 to reduce the risk of gastrointestinal adverse reactions [see Warnings and Precautions (5.6), Adverse Reactions (6.1)].
- If patients do not tolerate a dose during dosage escalation, consider delaying dosage escalation.
- The recommended maintenance dosage of WEGOVY tablets is 25 mg orally once daily.
- If patients do not tolerate the 25 mg once daily maintenance dosage, consider switching to WEGOVY injection 1.7 mg once weekly [see Dosage and Administration (2.5)].
- Do not take more than one tablet per day.

Table 2. Recommended Dosage of WEGOVY Tablets for Cardiovascular Risk Reduction or Weight Reduction in Adults

 | Days | Once Daily Tablet; Dosage
Starting Dosage | 1 through 30 | 1.5 mg
Dosage Escalation | 31 through 60 | 4 mg
Dosage Escalation | 61 through 90 | 9 mg
Maintenance Dosage | 91 and onward | 25 mg

2.4 Recommendations Regarding Missed Dose(s)

WEGOVY Injection

- If one dose of WEGOVY injection is missed and the next scheduled dose is:
- More than 2 days away, administer WEGOVY injection as soon as possible.
- Less than 2 days away do not administer the WEGOVY injection dose. Resume dosing on the regularly scheduled day of the week.
- If 2 or more consecutive doses of WEGOVY injection are missed, resume dosing as scheduled or, if needed, reinitiate WEGOVY injection and follow the dosage escalation schedule, which may reduce the occurrence of gastrointestinal adverse reactions associated with reinitiation of treatment [see Dosage and Administration (2.2)].

WEGOVY Tablets

If a dose of WEGOVY tablets is missed, skip the missed dose and take the next dose the following day.

2.5 Switching Between WEGOVY Injection and WEGOVY Tablets

Switching from WEGOVY Injection to WEGOVY Tablets

- Patients taking WEGOVY 2.4 mg injection for cardiovascular risk reduction or weight reduction in adults may switch to WEGOVY 25 mg tablets.
- One week after discontinuing WEGOVY 2.4 mg injection, initiate 25 mg of WEGOVY tablets orally once daily.

Switching from WEGOVY Tablets to WEGOVY Injection

- Patients may switch from WEGOVY 25 mg tablets to WEGOVY injection.
- The day after discontinuing WEGOVY tablets 25 mg once daily, initiate WEGOVY 2.4 mg subcutaneous injection once weekly. For patients who do not tolerate WEGOVY 25 mg tablets, consider switching to WEGOVY 1.7 mg injection.
- If additional weight reduction is needed in patients with type 2 diabetes mellitus treated with WEGOVY 25 mg tablets, consider switching to WEGOVY 1.7 mg injection and follow the recommended dosage escalation for WEGOVY injection. [see Dosage and Administration (2.2), Use in Specific Populations (8.6), and Clinical Pharmacology (12.3)].

3 DOSAGE FORMS AND STRENGTHS

Injection: clear, colorless solution available in 5 prefilled, disposable, single-dose pens:

- 0.25 mg/0.5 mL
- 0.5 mg/0.5 mL
- 1 mg/0.5 mL
- 1.7 mg/0.75 mL
- 2.4 mg/0.75 mL

Tablet: white to light yellow, round shaped debossed with the strength on one side and “novo” on the other side:

- 1.5 mg
- 4 mg
- 9 mg

Tablet: white to light yellow, oval shaped debossed with the strength on one side and “novo” on the other side:

- 25 mg

4 CONTRAINDICATIONS

WEGOVY is contraindicated in the following conditions:

- A personal or family history of MTC or in patients with MEN 2 [see Warnings and Precautions (5.1)].
- A prior serious hypersensitivity reaction to semaglutide or to any of the excipients in WEGOVY injection or WEGOVY tablet. Serious hypersensitivity reactions, including anaphylaxis and angioedema, have been reported with WEGOVY [see Warnings and Precautions (5.7)].

5 WARNINGS AND PRECAUTIONS

5.1 Risk of Thyroid C-Cell Tumors

In mice and rats, semaglutide caused a dose-dependent and treatment-duration-dependent increase in the incidence of thyroid C-cell tumors (adenomas and carcinomas) after lifetime exposure at clinically relevant plasma exposures [see Nonclinical Toxicology (13.1)]. It is unknown whether WEGOVY causes thyroid C-cell tumors, including MTC, in humans, as human relevance of semaglutide-induced rodent thyroid C-cell tumors has not been determined.

Cases of MTC in patients treated with liraglutide, another GLP-1 receptor agonist, have been reported in the postmarketing period; the data in these reports are insufficient to establish or exclude a causal relationship between MTC and GLP-1 receptor agonist use in humans.

WEGOVY is contraindicated in patients with a personal or family history of MTC or in patients with MEN 2. Counsel patients regarding the potential risk for MTC with the use of WEGOVY and inform them of symptoms of thyroid tumors (e.g., a mass in the neck, dysphagia, dyspnea, persistent hoarseness).

Routine monitoring of serum calcitonin or using thyroid ultrasound is of uncertain value for early detection of MTC in patients treated with WEGOVY. Such monitoring may increase the risk of unnecessary procedures, due to the low-test specificity for serum calcitonin and a high background incidence of thyroid disease. Significantly elevated serum calcitonin value may indicate MTC and patients with MTC usually have calcitonin values greater than 50 ng/L. If serum calcitonin is measured and found to be elevated, the patient should be further evaluated. Patients with thyroid nodules noted on physical examination or neck imaging should also be further evaluated.

5.2 Acute Pancreatitis

Acute pancreatitis, including fatal and non-fatal hemorrhagic or necrotizing pancreatitis, has been observed in patients treated with GLP-1 receptor agonists, including WEGOVY [see Adverse Reactions (6)]. After initiation of WEGOVY, observe patients carefully for signs and symptoms of acute pancreatitis, which may include persistent or severe abdominal pain (sometimes radiating to the back), and which may or may not be accompanied by nausea or vomiting. If pancreatitis is suspected, discontinue WEGOVY and initiate appropriate management.

5.3 Acute Gallbladder Disease

Treatment with WEGOVY is associated with an increased occurrence of cholelithiasis and cholecystitis. The incidence of cholelithiasis and cholecystitis was higher in WEGOVY injection-treated pediatric patients aged 12 years and older than in WEGOVY injection-treated adults. In randomized clinical trials in adults for weight reduction, cholelithiasis was reported by 1.6% of WEGOVY injection-treated patients and 0.7% of placebo injection-treated patients, and by 2.5% of WEGOVY tablet-treated patients and 1% of placebo tablet-treated patients. Cholecystitis was reported by 0.6% of WEGOVY injection-treated adult patients and 0.2% of placebo- treated patients. In a clinical trial in pediatric patients aged 12 years and older for weight reduction, cholelithiasis was reported by 3.8% of WEGOVY injection-treated patients and 0% placebo-treated patients. Cholecystitis was reported by 0.8% of WEGOVY injection-treated pediatric patients and 0% placebo-treated patients [see Adverse Reactions (6.1)].

Substantial or rapid weight loss can increase the risk of cholelithiasis; however, the incidence of acute gallbladder disease was greater in WEGOVY-treated patients than in placebo-treated patients, even after accounting for the degree of weight loss. If cholelithiasis is suspected, gallbladder studies and appropriate clinical follow-up are indicated.

5.4 Hypoglycemia

WEGOVY lowers blood glucose and can cause hypoglycemia.

In a trial of WEGOVY injection in adult patients with type 2 diabetes and body mass index (BMI) greater than or equal to 27 kg/m^2 for weight reduction (Study 3), hypoglycemia (defined as a plasma glucose less than 54 mg/dL) was reported in more patients treated with WEGOVY versus placebo [see Adverse Reaction (6.1)]. One episode of severe hypoglycemia (requiring the assistance of another person) was reported in one WEGOVY treated patient versus no placebo-treated patients [see Clinical Studies (14.2)].

In glycemic control clinical trials, the risk of hypoglycemia was increased when semaglutide injection or tablet was used concomitantly with insulin or an insulin secretagogue (e.g., sulfonylurea). Patients with diabetes mellitus taking WEGOVY in combination with insulin or an insulin secretagogue may have an increased risk of hypoglycemia, including severe hypoglycemia. The use of WEGOVY in patients with type 1 diabetes mellitus or in combination with insulin has not been evaluated.

Inform patients of the risk of hypoglycemia and educate them on the signs and symptoms of hypoglycemia. In patients with diabetes, monitor blood glucose prior to starting WEGOVY and during WEGOVY treatment. When initiating WEGOVY, consider reducing the dose of concomitantly administered insulin or insulin secretagogue to reduce the risk of hypoglycemia [see Drug Interactions (7.1)].

5.5 Acute Kidney Injury Due to Volume Depletion

There have been postmarketing reports of acute kidney injury, in some cases requiring hemodialysis, in patients treated with semaglutide [see Adverse Reactions (6)]. The majority of the reported events occurred in patients who experienced gastrointestinal adverse reactions leading to dehydration such as nausea, vomiting, or diarrhea [see Adverse Reactions (6)].

Monitor renal function in patients reporting adverse reactions to WEGOVY that could lead to volume depletion, especially during dosage initiation and escalation of WEGOVY.

5.6 Severe Gastrointestinal Adverse Reactions

Use of WEGOVY has been associated with gastrointestinal adverse reactions, sometimes severe [see Adverse Reactions (6.1)]. In clinical trials for adults for weight reduction, severe gastrointestinal adverse reactions were reported more frequently among patients receiving WEGOVY than placebo. Severe gastrointestinal adverse reactions were reported in 4.1% and 0.9% of WEGOVY-injection and placebo-treated patients, respectively, and in 2% of WEGOVY tablet-treated and 0% of placebo-treated patients, respectively. Severe gastrointestinal adverse reactions have also been reported postmarketing with GLP-1 receptor agonists.

WEGOVY is not recommended in patients with severe gastroparesis.

5.7 Hypersensitivity Reactions

Serious hypersensitivity reactions (e.g., anaphylaxis, angioedema) have been reported with WEGOVY. If hypersensitivity reactions occur, discontinue use of WEGOVY, treat promptly per standard of care, and monitor until signs and symptoms resolve. WEGOVY is contraindicated in patients with a prior serious hypersensitivity reaction to semaglutide or to any of the excipients in WEGOVY [see Adverse Reactions (6.2)].

Anaphylaxis and angioedema have been reported with other GLP-1 receptor agonists. Use caution in a patient with a history of anaphylaxis or angioedema with another GLP-1 receptor agonist because it is unknown whether such patients will be predisposed to these reactions with WEGOVY.

5.8 Diabetic Retinopathy Complications in Patients with Type 2 Diabetes

In a 2-year trial with semaglutide 0.5 mg and 1 mg once-weekly injection in adult patients with type 2 diabetes and high CV risk, diabetic retinopathy complications (which was a 4-component adjudicated endpoint) occurred in patients treated with semaglutide injection (3%) compared to placebo (1.8%). The absolute risk increase for diabetic retinopathy complications was larger among patients with a history of diabetic retinopathy at baseline (semaglutide injection 8.2%, placebo 5.2%) than among patients without a known history of diabetic retinopathy (semaglutide injection 0.7%, placebo 0.4%).

In a trial of adult patients with type 2 diabetes and BMI greater than or equal to 27 kg/m^2 for weight reduction (Study 3), diabetic retinopathy was reported by 4% of WEGOVY injection-treated patients and 2.7% placebo-treated patients [see Clinical Studies (14.2)].

In a glycemic control trial evaluating a dose comparable to the 9 mg dose and the 25 mg semaglutide tablet dose in patients with type 2 diabetes, a similar proportion of patients in each dose group reported diabetic retinopathy related adverse reactions during the trial; 1.3% and 1.9% of patients in the 9 mg and 25 mg semaglutide group, respectively, reported moderate-severe non-proliferative diabetic retinopathy events, and 0% and 0.4% reported proliferative retinopathy events, respectively.

Rapid improvement in glucose control has been associated with a temporary worsening of diabetic retinopathy. The effect of long-term glycemic control with semaglutide on diabetic retinopathy complications has not been studied. Patients with a history of diabetic retinopathy should be monitored for progression of diabetic retinopathy.

5.9 Heart Rate Increase

Treatment with WEGOVY was associated with increases in resting heart rate. Mean increases in resting heart rate of 1 to 4 beats per minute (bpm) were observed in WEGOVY injection-treated adult patients compared to placebo in clinical trials for weight reduction. More adult patients treated with WEGOVY injection compared with placebo had maximum changes from baseline at any visit of 10 to 19 bpm (41% versus 34%, respectively) and 20 bpm or more (26% versus 16%, respectively). In a clinical trial in pediatric patients aged 12 years and older with normal baseline heart rate, more patients treated with WEGOVY injection compared to placebo had maximum changes in heart rate of 20 bpm or more (54% versus 39%) [see Adverse Reactions (6.1)]. Findings were similar in a trial with the WEGOVY tablets.

Monitor heart rate at regular intervals consistent with usual clinical practice. Instruct patients to inform their healthcare providers of palpitations or feelings of a racing heartbeat while at rest during WEGOVY treatment. If patients experience a sustained increase in resting heart rate, discontinue WEGOVY.

5.10 Suicidal Behavior and Ideation

Suicidal behavior and ideation have been reported in clinical trials with other weight management products. Monitor patients treated with WEGOVY for the emergence or worsening of depression, suicidal thoughts or behavior, and/or any unusual changes in mood or behavior. Discontinue WEGOVY in patients who experience suicidal thoughts or behaviors. Avoid WEGOVY in patients with a history of suicidal attempts or active suicidal ideation.

5.11 Pulmonary Aspiration During General Anesthesia or Deep Sedation

WEGOVY delays gastric emptying [see Clinical Pharmacology (12.2)]. There have been rare postmarketing reports of pulmonary aspiration in patients receiving GLP-1 receptor agonists undergoing elective surgeries or procedures requiring general anesthesia or deep sedation who had residual gastric contents despite reported adherence to preoperative fasting recommendations.

Available data are insufficient to inform recommendations to mitigate the risk of pulmonary aspiration during general anesthesia or deep sedation in patients taking WEGOVY, including whether modifying preoperative fasting recommendations or temporarily discontinuing WEGOVY could reduce the incidence of retained gastric contents. Instruct patients to inform healthcare providers prior to any planned surgeries or procedures if they are taking WEGOVY.

6 ADVERSE REACTIONS

The following serious adverse reactions are described below or elsewhere in the prescribing information:

- Risk of Thyroid C-Cell Tumors [see Warnings and Precautions (5.1)]
- Acute Pancreatitis [see Warnings and Precautions (5.2)]
- Acute Gallbladder Disease [see Warnings and Precautions (5.3)]
- Hypoglycemia [see Warnings and Precautions (5.4)]
- Acute Kidney Injury due to Volume Depletion [see Warnings and Precautions (5.5)]
- Severe Gastrointestinal Adverse Reactions [see Warnings and Precautions (5.6)]
- Hypersensitivity Reactions [see Warnings and Precautions (5.7)]
- Diabetic Retinopathy Complications in Patients with Type 2 Diabetes [see Warnings and Precautions (5.8)]
- Heart Rate Increase [see Warnings and Precautions (5.9)]
- Suicidal Behavior and Ideation [see Warnings and Precautions (5.10)]
- Pulmonary Aspiration During General Anesthesia or Deep Sedation [see Warnings and Precautions (5.11)]

6.1 Clinical Trials Experience

Because clinical trials are conducted under widely varying conditions, adverse reaction rates observed in the clinical trials of a drug cannot be directly compared to rates in the clinical studies of another drug and may not reflect the rates observed in practice.

Adverse Reactions in Clinical Trials in Adults with Obesity or Overweight for Weight Reduction

WEGOVY 2.4 mg Subcutaneous Weekly Dosage

WEGOVY was evaluated for safety in 3 randomized, double-blind, placebo-controlled trials that included 2,116 adult patients with obesity or overweight treated with 2.4 mg WEGOVY for up to 68 weeks and a 7-week off-drug follow-up period [see Clinical Studies (14.2)]. Baseline characteristics included a mean age of 48 years, 71% female, 72% White, 14% Asian, 9% Black or African American, and 5% reported as other or unknown; and 85% were not Hispanic or Latino ethnicity, 13% were Hispanic or Latino ethnicity, and 2% reported as unknown. The baseline characteristics were 42% with hypertension, 19% with type 2 diabetes, 43% with dyslipidemia, 28% with a BMI greater than 40 kg/m^2, and 4% with CV disease.

In these clinical trials, 6.8% of patients treated with 2.4 mg WEGOVY and 3.2% of patients treated with placebo permanently discontinued treatment as a result of adverse reactions. The most common adverse reactions leading to discontinuation were nausea (1.8% versus 0.2%), vomiting (1.2% versus 0%), and diarrhea (0.7% versus 0.1%) for WEGOVY and placebo, respectively.

Adverse reactions reported in clinical trials in adults and greater than or equal to 2% of WEGOVY-treated patients and more frequently than in placebo-treated patients are shown in Table 3.

Table 3. Adverse Reactions (≥2% and Greater Than Placebo) in WEGOVY Injection-treated Adults with Obesity or Overweight for Weight Reduction

 | Placebo N=1,261 % | WEGOVY Injection (2.4 mg once weekly) N=2,116 %
Nausea | 16 | 44
Diarrhea | 16 | 30
Vomiting | 6 | 24
Constipation | 11 | 24
Abdominal Paina | 10 | 20
Headache | 10 | 14
Fatigueb | 5 | 11
Dyspepsia | 3 | 9
Dizziness | 4 | 8
Abdominal Distension | 5 | 7
Eructation | <1 | 7
Hypoglycemia in T2DMc | 2 | 6
Flatulence | 4 | 6
Gastroenteritis | 4 | 6
Gastroesophageal Reflux Disease | 3 | 5
Gastritisd | 1 | 4
Gastroenteritis Viral | 3 | 4
Hair Loss | 1 | 3
Dysesthesiae | 1 | 2

a Includes abdominal pain, abdominal pain upper, abdominal pain lower, gastrointestinal pain, abdominal tenderness, abdominal discomfort and epigastric discomfort

b Includes fatigue and asthenia

c Defined as blood glucose <54 mg/dL with or without symptoms of hypoglycemia or severe hypoglycemia (requiring the assistance of another person) in patients with type 2 diabetes not on concomitant insulin (Study 3, WEGOVY N=403, Placebo N=402). See text below for further information regarding hypoglycemia in patients with and without type 2 diabetes. T2DM = type 2 diabetes mellitus
d Includes chronic gastritis, gastritis, gastritis erosive, and reflux gastritis
e Includes paresthesia, hyperesthesia, burning sensation, allodynia, dysesthesia, skin burning sensation, pain of skin, and sensitive skin

In a CV outcomes trial, 8,803 patients were exposed to WEGOVY injection for a median of 37.3 months and 8,801 patients were exposed to placebo for a median of 38.6 months [see Clinical Studies (14.1)]. Safety data collection was limited to serious adverse events (including death), adverse events leading to discontinuation, and adverse events of special interest. Sixteen percent (16%) of WEGOVY injection-treated patients and 8% of placebo-treated patients, respectively, discontinued study drug due to an adverse event. Additional information from this trial is included in subsequent sections below when relevant.

WEGOVY Tablet 25 mg Oral Daily Dosage

WEGOVY tablet was evaluated for safety in a randomized, double-blind, placebo-controlled trial that included 204 adult patients with obesity or overweight and at least one weight-related comorbidity, treated with WEGOVY tablet for up to 64 weeks and a 7-week off drug follow-up period (Study 7) [see Clinical Studies (14.2)]. Patients with type 2 diabetes mellitus were excluded. Baseline characteristics included a mean age of 48 years, 75.6% were female, 92.7% were White, 0.5% were Asian, 6.3% were Black or African American, and 8.3% were Hispanic or Latino ethnicity. Mean baseline body weight was 106.4 kg and mean BMI was 37.5 kg/m^2. The baseline characteristics were 44% with hypertension, 31% with dyslipidemia, 27% with a BMI greater than 40 kg/m^2, and 1.5% with coronary artery disease.

In the clinical trial, 6.9% of patients treated with WEGOVY 25 mg tablets and 5.9% patients treated with placebo permanently discontinued treatment as a result of adverse reactions. The most common event type leading to discontinuation was gastrointestinal adverse reactions reported in 3.4% with WEGOVY tablets and 2% with placebo.

In the clinical trial with WEGOVY tablets, the types and frequency of common adverse reactions were similar to those listed in Table 3.

Adverse Reactions in a Clinical Trial of Pediatric Patients Aged 12 Years and Older with Obesity Treated with WEGOVY Injection for Weight Reduction

WEGOVY injection was evaluated in a 68-week, double-blind, randomized, parallel group, placebo-controlled, multi-center trial in 201 pediatric patients aged 12 years and older with obesity [see Clinical Studies (14.3)]. Baseline characteristics included a mean age of 15.4 years; 38% of patients were male; 79% were White, 8% were Black or African American, 2% were Asian, and 11% were of other or unknown race; and 11% were of Hispanic or Latino ethnicity. The mean baseline body weight was 107.5 kg, and mean BMI was 37 kg/m^2.

Table 4 shows adverse reactions reported in greater than or equal to 3% of WEGOVY injection-treated pediatric patients and more frequently than in the placebo group from a study in pediatric patients aged 12 years and older.

Table 4. Adverse Reactions (≥3% and Greater than Placebo) in WEGOVY Injection-treated Pediatric Patients Aged 12 Years and Older with Obesity for Weight Reduction

 | Placebo N=67 % | WEGOVY Injection (2.4 mg once weekly) N=133 %
Nausea | 18 | 42
Vomiting | 10 | 36
Diarrhea | 19 | 22
Headache | 16 | 17
Abdominal Pain | 6 | 15
Nasopharyngitis | 10 | 12
Dizziness | 3 | 8
Gastroenteritis | 3 | 7
Constipation | 2 | 6
Gastroesophageal Reflux Disease | 2 | 4
Sinusitis | 2 | 4
Urinary tract infection | 2 | 4
Ligament sprain | 2 | 4
Anxiety | 2 | 4
Hair Loss | 0 | 4
Cholelithiasis | 0 | 4
Eructation | 0 | 4
Influenza | 0 | 3
Rash | 0 | 3
Urticaria | 0 | 3

Adverse Reactions in Clinical Trials in Adults with MASH Treated with WEGOVY Injection

The safety of WEGOVY injection was evaluated in a randomized, double-blind, placebo-controlled trial (Study 9) that included 1,195 adult patients with MASH, including 800 patients who were exposed to WEGOVY for a median of 95.3 weeks and 395 patients who were exposed to placebo for a median of 83.1 weeks [see Clinical Studies (14.4)].

The most commonly reported adverse reactions were consistent with the other approved WEGOVY indications (see Table 3). There is limited information in patients with MASH and a BMI <25 kg/m^2. Additional information from the MASH trial is included in subsequent sections when notable. Unless indicated, the incidence of the adverse reactions in MASH patients was similar to other approved indications.

Other Adverse Reactions in Adults and/or Pediatric Patients Treated with WEGOVY Injection or WEGOVY Tablets

Acute Gallbladder Disease

In WEGOVY clinical trials in adults for weight reduction, cholelithiasis was reported by 1.6% of WEGOVY injection-treated patients and 0.7% of placebo-treated patients and by 2.5% of WEGOVY tablet-treated patients and 1% of placebo tablet-treated patients. Cholecystitis was reported by 0.6% of WEGOVY injection-treated adult patients and 0.2% of placebo-treated patients. In a clinical trial in pediatric patients aged 12 years and older for weight reduction [see Clinical Studies (14.3)], cholelithiasis was reported by 3.8% of WEGOVY injection-treated patients and 0% placebo-treated patients. Cholecystitis was reported by 0.8% of WEGOVY injection-treated pediatric patients and 0% placebo-treated patients.

Hypoglycemia

Patients with Type 2 Diabetes

In a trial of adult patients with type 2 diabetes and BMI greater than or equal to 27 kg/m^2 for weight reduction, clinically significant hypoglycemia (defined as a plasma glucose less than 54 mg/dL) was reported in 6.2% of WEGOVY injection-treated patients versus 2.5% of placebo-treated patients. A higher rate of clinically significant hypoglycemic episodes was reported with WEGOVY injection (semaglutide 2.4 mg) versus semaglutide 1 mg injection (10.7 vs. 7.2 episodes per 100 patient years of exposure, respectively); the rate in the placebo-treated group was 3.2 episodes per 100 patient years of exposure. In addition, one episode of severe hypoglycemia requiring intravenous glucose was reported in a WEGOVY injection-treated patient versus none in placebo-treated patients. The risk of hypoglycemia was increased when WEGOVY was used with a sulfonylurea.

In a glycemic control trial evaluating a dose comparable to the 9 mg dose and the 25 mg semaglutide tablet dose in patients with type 2 diabetes not on insulin, clinically significant hypoglycemia was reported in similar proportions of subjects in both treatment groups.

Patients without Type 2 Diabetes

Episodes of hypoglycemia have been reported with GLP-1 receptor agonists in adult patients without type 2 diabetes mellitus. In WEGOVY clinical trials in adult patients without type 2 diabetes mellitus for weight reduction, there was no systematic capturing or reporting of hypoglycemia.

In a CV outcomes trial in adult patients without type 2 diabetes, 3 episodes of serious hypoglycemia were reported in WEGOVY injection-treated patients versus 1 episode in placebo. Patients with a history of bariatric surgery (a risk factor for hypoglycemia) had more events of serious hypoglycemia while taking WEGOVY injection (2.3%, 2/87) than placebo (0%, 0/97).

Retinal Disorders in Patients with Type 2 Diabetes

In a trial of adult patients with type 2 diabetes and BMI greater than or equal to 27 kg/m^2 for weight reduction, retinal disorders were reported by 6.9% of patients treated with WEGOVY injection (semaglutide 2.4 mg), 6.2% of patients treated with semaglutide 1 mg, and 4.2% of patients treated with placebo. The majority of events were reported as diabetic retinopathy (4%, 2.7%, and 2.7%, respectively) and non-proliferative retinopathy (0.7%, 0%, and 0%, respectively).

In a glycemic control trial evaluating the 9 mg and 25 mg semaglutide tablet doses in patients with type 2 diabetes, a similar proportion of patients in each dose group reported diabetic retinopathy related adverse reactions during the trial; 1.3% and 1.9% of patients in the 9 mg and 25 mg semaglutide group, respectively, reported moderate-severe non-proliferative diabetic retinopathy events, and 0% and 0.4% reported proliferative retinopathy events, respectively.

In a 2-year trial with semaglutide 0.5 mg and 1 mg once-weekly injection in adult patients with type 2 diabetes and high cardiovascular risk, diabetic retinopathy complications (which was a 4-component adjudicated endpoint) occurred in patients treated with semaglutide injection (3%) compared to placebo (1.8%). The absolute risk increase for diabetic retinopathy complications was larger among patients with a history of diabetic retinopathy at baseline (semaglutide injection 8.2%, placebo 5.2%) than among patients without a known history of diabetic retinopathy (semaglutide injection 0.7%, placebo 0.4%).

Gastrointestinal Adverse Reactions

In clinical trials in adults for weight reduction, 73% of WEGOVY injection-treated patients and 47% of patients receiving placebo reported gastrointestinal adverse reactions, including severe reactions that were reported more frequently among patients receiving WEGOVY injection (4.1%) than placebo (0.9%). The most frequently reported reactions were nausea (44% vs. 16%), vomiting (25% vs. 6%), and diarrhea (30% vs. 16%). Other reactions that occurred at a higher incidence among WEGOVY injection-treated adult patients included dyspepsia, abdominal pain, abdominal distension, eructation, flatulence, gastroesophageal reflux disease, gastritis, hemorrhoids, and hiccups. These reactions were most frequently reported during dosage escalation.

Severe gastrointestinal adverse reactions were reported in 2% of WEGOVY tablet-treated and 0% of placebo-treated patients, respectively.

In the pediatric clinical trial for weight reduction, 62% of WEGOVY injection-treated patients and 42% of placebo-treated patients reported gastrointestinal adverse reactions. The most frequently reported reactions were nausea (42% vs. 18%), vomiting (36% vs. 10%), and diarrhea (22% vs. 19%). Other gastrointestinal-related reactions that occurred at a higher incidence than placebo among WEGOVY injection-treated pediatric patients included abdominal pain, constipation, eructation, gastroesophageal reflux disease, dyspepsia, and flatulence.

Permanent discontinuation of treatment as a result of a gastrointestinal adverse reaction occurred in 4.3% of WEGOVY injection-treated adult patients versus 0.7% of placebo-treated patients. In a pediatric clinical trial for weight reduction, 2.3% of patients treated with WEGOVY injection versus 1.5% of patients who received placebo discontinued treatment as a result of gastrointestinal adverse reactions.

Other Adverse Reactions in Adults and/or Pediatric Patients Treated with WEGOVY Injection

The below adverse reactions are applicable for both WEGOVY injection and WEGOVY tablets and include descriptions of WEGOVY injection clinical trial data, where relevant. The safety and effectiveness of WEGOVY tablets have not been established in pediatric patients or patients with MASH.

Acute Pancreatitis

In WEGOVY clinical trials in adults for weight reduction, acute pancreatitis was confirmed by adjudication in 4 WEGOVY-treated patients (0.2 cases per 100 patient years) and 1 in placebo-treated patients (less than 0.1 cases per 100 patient years). One additional case of acute pancreatitis was confirmed in a patient treated with WEGOVY in another clinical trial.

Acute Kidney Injury

Acute kidney injury occurred in clinical trials for weight reduction in 7 adult patients (0.4 cases per 100 patient years) receiving WEGOVY versus 4 patients (0.2 cases per 100 patient years of exposure) receiving placebo. Some of these adverse reactions occurred in association with gastrointestinal adverse reactions or dehydration. In addition, 2 patients treated with WEGOVY had acute kidney injury with dehydration in other clinical trials. The risk of renal adverse reactions with WEGOVY was increased in adult patients with a history of renal impairment (trials included 65 patients with a history of moderate or severe renal impairment at baseline), and occurred more frequently during dose titration.

Increase in Heart Rate

Mean increases in resting heart rate of 1 to 4 beats per minute (bpm) were observed with routine clinical monitoring in WEGOVY-treated adult patients compared to placebo in clinical trials for weight reduction. In weight reduction trials in which adult patients were randomized prior to dose-escalation, more patients treated with WEGOVY, compared with placebo, had maximum changes from baseline at any visit of 10 to 19 bpm (41% versus 34%, respectively) and 20 bpm or more (26% versus 16%, respectively). In a clinical trial for weight reduction in pediatric patients aged 12 years and older with normal baseline heart rate, more patients treated with WEGOVY compared to placebo had maximum changes in heart rate of 20 bpm or more (54% versus 39%).

Hypotension and Syncope

Adverse reactions related to hypotension (hypotension, orthostatic hypotension, and decreased blood pressure) were reported in 1.3% of WEGOVY-treated adult patients versus 0.4% of placebo-treated patients and syncope was reported in 0.8% of WEGOVY-treated patients versus 0.2% of placebo-treated patients in clinical trials for weight reduction. Some reactions were related to gastrointestinal adverse reactions and volume loss associated with WEGOVY. Hypotension and orthostatic hypotension were more frequently seen in patients on concomitant antihypertensive therapy. In a clinical trial in pediatric patients aged 12 years and older for weight reduction, hypotension was reported in 2.3% of WEGOVY-treated patients versus 0% in placebo-treated patients.

Appendicitis

Appendicitis (including perforated appendicitis) occurred in 10 (0.5%) WEGOVY-treated adult patients and 2 (0.2%) patients receiving placebo in clinical trials for weight reduction.

Injection Site Reactions

In clinical trials in adults for weight reduction, 1.4% of WEGOVY-treated patients and 1% of patients receiving placebo experienced injection site reactions (including injection site pruritus, erythema, inflammation, induration, and irritation).

Hypersensitivity Reactions

Serious hypersensitivity reactions (e.g., anaphylaxis, angioedema) have been reported with WEGOVY.

In a pediatric clinical trial for weight reduction, rash was reported in 3% of WEGOVY-treated patients and 0% of placebo-treated patients, and urticaria was reported in 3% of WEGOVY-treated patients and 0% of placebo-treated patients.

In adult clinical trials for weight reduction, allergic reactions occurred in 16% (8/50) of WEGOVY-treated patients with anti-semaglutide antibodies and in 7% (114/1659) of WEGOVY-treated patients who did not develop anti-semaglutide antibodies [see Clinical Pharmacology (12.6)].

Fractures

In the CV outcomes trial in adults, more fractures of the hip and pelvis were reported on WEGOVY than on placebo in female patients: 1% (24/2,448) vs. 0.2% (5/2,424), and in patients ages 75 years and older: 2.4% (17/703) vs. 0.6% (4/663), respectively.

In a clinical trial in adults with MASH, fractures occurred in 4.4% of WEGOVY-treated patients (2.6 cases per 100 patient years) compared to 3.3% of placebo-treated patients (2 cases per 100 patient years). Fractures were reported in both males and females with a median age of 61 years (range, 44 to 75).

Urolithiasis

In a CV outcomes trial, 1.2% of WEGOVY-treated patients and 0.8% of patients receiving placebo reported urolithiasis, including serious reactions that were reported more frequently among patients receiving WEGOVY (0.6%) than placebo (0.4%).

Dysgeusia

In clinical trials in adults for weight reduction, 1.7% of WEGOVY-treated patients and 0.5% of placebo-treated patients reported dysgeusia.

Other Adverse Reactions in Adult Patients Treated with WEGOVY Tablets for Weight Reduction

Dysesthesia

In a clinical trial with WEGOVY tablets, 4.9% of WEGOVY-treated patients and no placebo-treated patients reported dysesthesia adverse reactions, with preferred terms including sensitive skin, hyperesthesia, paresthesia, allodynia, and skin burning sensation.

Laboratory Abnormalities in Adults and/or Pediatric Patients Treated with WEGOVY Injection

The below laboratory abnormalities are applicable for both WEGOVY injection and WEGOVY tablets and include descriptions of WEGOVY injection clinical trial data, where relevant. The safety and effectiveness of WEGOVY tablets have not been established in pediatric patients or patients with MASH.

Amylase and Lipase

Adult and pediatric patients treated with WEGOVY had a mean increase from baseline in amylase of 15% to 16% and lipase of 39% in clinical trials for weight reduction. These changes were not observed in the placebo group.

In a clinical trial in adults with MASH, increases in lipase greater than 3 times the upper limit of normal (ULN) occurred in 4.7% (35/750) of WEGOVY-treated patients compared with 1.3% (5/374) of placebo-treated patients. The clinical significance of elevations in lipase or amylase with WEGOVY is unknown in the absence of other signs and symptoms of pancreatitis.

Liver Tests

In a pediatric clinical trial for weight reduction, increases in alanine aminotransferase (ALT) greater than or equal to 5 times the ULN were observed in 4 (3%) WEGOVY-treated patients compared with 0% of placebo-treated patients. In some patients, increases in ALT and AST were associated with other confounding factors (such as gallstones). In the CV outcomes trial in adults, increases in total bilirubin greater than or equal to 3 times the ULN were observed in 0.3% (30/8,585) of WEGOVY-treated patients versus 0.2% (14/8,579) of placebo-treated patients.

6.2 Postmarketing Experience

The following adverse reactions have been reported during post-approval use of semaglutide, the active ingredient of WEGOVY. Because these reactions are reported voluntarily from a population of uncertain size, it is not always possible to reliably estimate their frequency or establish a causal relationship to drug exposure.

Gastrointestinal Disorders: acute pancreatitis and necrotizing pancreatitis, sometimes resulting in death; ileus, intestinal obstruction, severe constipation including fecal impaction

Hypersensitivity: anaphylaxis, angioedema, rash, urticaria

Pulmonary: Pulmonary aspiration has occurred in patients receiving GLP-1 receptor agonists undergoing elective surgeries or procedures requiring general anesthesia or deep sedation

Renal and Urinary Disorders: acute kidney injury

7 DRUG INTERACTIONS

7.1 Concomitant Use with Insulin or an Insulin Secretagogue (e.g., Sulfonylurea)

WEGOVY lowers blood glucose and can cause hypoglycemia. The risk of hypoglycemia is increased when WEGOVY is used concomitantly with insulin or insulin secretagogues (e.g., sulfonylureas). The addition of WEGOVY in patients treated with insulin has not been evaluated.

When initiating WEGOVY, consider reducing the dose of concomitantly administered insulin secretagogue or insulin to reduce the risk of hypoglycemia [see Warnings and Precautions (5.4), Adverse Reactions (6.1)].

7.2 Oral Medications

WEGOVY causes a delay of gastric emptying and thereby has the potential to impact the absorption of concomitantly administered oral medications. In clinical pharmacology trials with semaglutide 1 mg once weekly injection, semaglutide did not affect the absorption of orally administered medications [see Clinical Pharmacology (12.3)]. In a drug interaction study with the semaglutide tablet, levothyroxine exposure was increased 33% (90% CI: 1.25-1.42). Monitor the effects of oral medications concomitantly administered with WEGOVY. Consider increased clinical or laboratory monitoring for medications that have a narrow therapeutic index or that require clinical monitoring.

8 USE IN SPECIFIC POPULATIONS

8.1 Pregnancy

Pregnancy Exposure Registry

There is a pregnancy exposure registry that monitors pregnancy outcomes in women exposed to semaglutide during pregnancy. Pregnant women exposed to WEGOVY and healthcare providers are encouraged to contact Novo Nordisk at 1-877-390-2760 or www.wegovypregnancyregistry.com.

Risk Summary

Based on animal reproduction studies, there may be potential risks to the fetus from exposure to semaglutide during pregnancy. Available pharmacovigilance data and data from clinical trials with WEGOVY use in pregnant patients are insufficient to establish a drug-associated risk of major birth defects, miscarriage or adverse maternal or fetal outcomes.

Weight loss offers no benefit to a pregnant patient and may cause fetal harm. When a pregnancy is recognized, advise the pregnant patient of the risk to a fetus, and discontinue WEGOVY (see Clinical Considerations).

There may be risks to the mother and fetus related to underlying MASH with advanced liver fibrosis (see Clinical Considerations). Whether semaglutide treatment during pregnancy reduces these risks is unknown. WEGOVY for the treatment of MASH should be used during pregnancy only if the potential benefit justifies the potential risk to the fetus.

In pregnant rats administered semaglutide during organogenesis, embryofetal mortality, structural abnormalities and alterations to growth occurred at maternal exposures below the maximum recommended human dose (MRHD) based on AUC. In rabbits and cynomolgus monkeys administered semaglutide during organogenesis, early pregnancy losses and structural abnormalities were observed at below the MRHD (rabbit) and greater than or equal to 2-fold the MRHD (monkey). These findings coincided with a marked maternal body weight loss in both animal species (see Data).

The background risk of major birth defects and miscarriage for the indicated populations are unknown. In the U.S. general population, the estimated background risk of major birth defects and miscarriage in clinically recognized pregnancies is 2% to 4% and 15% to 20%, respectively.

Clinical Considerations

Disease-associated maternal and/or embryo/fetal risk

Appropriate weight gain based on pre-pregnancy weight is currently recommended for all pregnant patients, including those who already have overweight or obesity, because of the obligatory weight gain that occurs in maternal tissues during pregnancy.

There may be risks to the mother and fetus related to MASH with advanced liver fibrosis, such as increased risks of gestational diabetes, hypertensive complications, preterm birth, and postpartum hemorrhage. The effect of semaglutide on these risks is unknown.

Data

Animal Data

In a combined fertility and embryofetal development study in rats, subcutaneous doses of 0.01, 0.03, and 0.09 mg/kg/day (0.04-, 0.1-, and 0.4-fold the MRHD) were administered to males for 4 weeks prior to and throughout mating and to females for 2 weeks prior to mating, and throughout organogenesis to Gestation Day 17. In parental animals, pharmacologically mediated reductions in body weight gain and food consumption were observed at all dose levels. In the offspring, reduced growth and fetuses with visceral (heart blood vessels) and skeletal (cranial bones, vertebra, ribs) abnormalities were observed at the human exposure.

In an embryofetal development study in pregnant rabbits, subcutaneous doses of 0.001, 0.0025, or 0.0075 mg/kg/day (0.01-, 0.1-, and 0.9-fold the MRHD) were administered throughout organogenesis from Gestation Day 6 to 19. Pharmacologically mediated reductions in maternal body weight gain and food consumption were observed at all dose levels. Early pregnancy losses and increased incidences of minor visceral (kidney, liver) and skeletal (sternebra) fetal abnormalities were observed at greater than or equal to 0.0025 mg/kg/day, at clinically relevant exposures.

In an embryofetal development study in pregnant cynomolgus monkeys, subcutaneous doses of 0.015, 0.075, and 0.15 mg/kg twice weekly (0.4-, 2-, and 6-fold the MRHD) were administered throughout organogenesis, from Gestation Day 16 to 50. Pharmacologically mediated, marked initial maternal body weight loss and reductions in body weight gain and food consumption coincided with the occurrence of sporadic abnormalities (vertebra, sternebra, ribs) at greater than or equal to 0.075 mg/kg twice weekly (greater than or equal to 2 times human exposure).

In a pre- and postnatal development study in pregnant cynomolgus monkeys, subcutaneous doses of 0.015, 0.075, and 0.15 mg/kg twice weekly (0.2-, 1-, and 3-fold the MRHD) were administered from Gestation Day 16 to 140. Pharmacologically mediated marked initial maternal body weight loss and reductions in body weight gain and food consumption coincided with an increase in early pregnancy losses and led to delivery of slightly smaller offspring at greater than or equal to 0.075 mg/kg twice weekly (greater than or equal to 1-time human exposure).

Salcaprozate sodium (SNAC), an absorption enhancer in WEGOVY tablets, crosses the placenta and reaches fetal tissues in rats. In a pre- and postnatal development study in pregnant Sprague Dawley rats, SNAC was administered orally at 1,000 mg/kg/day (exposure levels were not measured) on Gestation Day 7 through lactation Day 20. An increase in gestation length, an increase in the number of stillbirths and a decrease in pup viability were observed.

8.2 Lactation

Risk Summary

WEGOVY Oral Tablets

Data from a clinical lactation study with semaglutide oral tablet formulation reported semaglutide concentrations below the lower limit of quantification in human milk. However, SNAC and/or its metabolites are present in human milk. Since the activity of enzymes involved in SNAC clearance may be lower in infants compared to adults, higher SNAC plasma levels may occur in neonates and infants. Because of the unknown potential for serious adverse reactions in the breastfed infant due to the possible accumulation of SNAC, and because there are alternative formulations of semaglutide that do not contain SNAC that can be used during lactation, advise patients that breastfeeding is not recommended during treatment with WEGOVY tablets.

WEGOVY Subcutaneous Injection

There are no data on the presence of subcutaneously administered semaglutide or its metabolites in human milk, the effects on the breastfed infant, or the effects on milk production. WEGOVY subcutaneous injection does not contain the SNAC metabolites.

The developmental and health benefits of breastfeeding should be considered along with the mother’s clinical need for WEGOVY and any potential adverse effects on the breastfed infant from WEGOVY or from the underlying maternal condition.

8.3 Females and Males of Reproductive Potential

Because of the potential for fetal harm, discontinue WEGOVY in patients at least 2 months before they plan to become pregnant to account for the long half-life of semaglutide [see Use in Specific Populations (8.1)].

8.4 Pediatric Use

The safety and effectiveness of WEGOVY injection in combination with a reduced-calorie diet and increased physical activity to reduce excess body weight and maintain weight reduction long term in pediatric patients aged 12 years and older with obesity have been established. Use of WEGOVY injection for this indication is supported by a 68-week, double-blind, placebo-controlled clinical trial in 201 pediatric patients aged 12 years and older with a BMI corresponding to ≥95th percentile for age and sex [see Clinical Studies (14.3)] and from trials in adult patients with obesity [see Clinical Studies (14.2)]. Use of the 1.7 mg once weekly maintenance dosage of WEGOVY injection in pediatric patients is also supported by additional exposure-efficacy and safety analyses in pooled adult and pediatric patients.

Adverse reactions with WEGOVY-injection treatment in pediatric patients aged 12 years and older were generally similar to those reported in adults. Pediatric patients aged 12 years and older treated with WEGOVY injection had greater incidences of cholelithiasis, cholecystitis, hypotension, rash, and urticaria compared to adults treated with WEGOVY [see Adverse Reactions (6.1)].

Although there was an increased frequency of hypoglycemia in adults with type 2 diabetes with obesity or overweight treated with WEGOVY injection, there are insufficient data to determine if the risk of hypoglycemia is higher in WEGOVY-treated pediatric patients with type 2 diabetes with obesity. Inform pediatric patients of the risk of hypoglycemia and educate them on the signs and symptoms of hypoglycemia. In pediatric patients aged 12 years and older with type 2 diabetes, monitor blood glucose prior to starting WEGOVY injection and during treatment. When initiating WEGOVY injection in pediatric patients aged 12 years and older with type 2 diabetes, consider reducing the dosage of concomitantly administered insulin secretagogue (such as sulfonylureas) or insulin to reduce the risk of hypoglycemia [see Warnings and Precautions (5.4)].

The safety and effectiveness of WEGOVY injection have not been established in pediatric patients:

- to reduce the risk of major adverse CV events. Clinical trials for this indication are highly impracticable because of the low prevalence of the condition in pediatric patients.
- to reduce excess body weight and maintain weight reduction long term in those less than 12 years of age.
- for the treatment of noncirrhotic MASH.

The safety and effectiveness of WEGOVY tablets have not been established in pediatric patients.

8.5 Geriatric Use

In the WEGOVY injection clinical trials for weight reduction and long-term maintenance, 233 (9%) WEGOVY injection-treated patients were aged 65 to less than 75 years and 23 (1%) WEGOVY injection-treated patients were aged 75 years and older [see Clinical Studies (14.2)]. In a WEGOVY tablets clinical trial for weight reduction and long-term maintenance, 16 (8%) WEGOVY tablets-treated patients were aged 65 to less than 75 years and 5 (2%) WEGOVY tablet-treated patients were aged 75 years and older [see Clinical Studies (14.2)].

In a CV outcomes trial, 2,656 (30%) WEGOVY injection-treated patients were aged 65 to 75 years and 703 (8%) WEGOVY injection-treated patients were aged 75 years and older [see Clinical Studies (14.1)]. No overall difference in the effectiveness was observed between patients aged 65 years and older and younger adult patients. In the CV outcomes trial, patients aged 75 years and older reported more hip and pelvis fractures in the WEGOVY injection-treated patients than placebo-treated patients. Patients aged 75 years and older (WEGOVY injection-treated and placebo-treated) reported more serious adverse reactions overall compared to younger adult patients [see Adverse Reactions (6.1)].

In the clinical trial in patients with MASH, of the 534 patients randomized to WEGOVY injection, 138 (26%) were aged 65 years and older and 13 (2%) were aged 75 years and older [see Clinical Studies (14.4)]. No overall differences in safety or effectiveness of WEGOVY injection have been observed between patients 65 years of age and older and younger adult patients with MASH.

8.6 Type 2 Diabetes Mellitus

WEGOVY tablets have not been studied for weight reduction in adults with type 2 diabetes and obesity or overweight [see Clinical Studies (14.2)].

Administration of WEGOVY injection resulted in less weight reduction in patients with type 2 diabetes and obesity or overweight compared to those without type 2 diabetes and obesity or overweight [see Clinical Studies (14.2)].

In patients without type 2 diabetes, the average semaglutide blood concentrations following administration of WEGOVY 25 mg tablets once daily or WEGOVY 2.4 mg injection once weekly were similar. In patients with type 2 diabetes, the average semaglutide blood concentrations following administration of WEGOVY 25 mg tablets once daily were lower than the average semaglutide blood concentrations following use of WEGOVY 2.4 mg injection once weekly [see Clinical Pharmacology (12.3)]. The lower semaglutide blood concentrations after administration of WEGOVY tablets in patients with type 2 diabetes may be associated with reductions in absolute bioavailability.

Given the differences in average semaglutide blood concentrations after administration of WEGOVY tablets and WEGOVY injection, and the higher variability in semaglutide blood concentrations after administration of WEGOVY tablets in all patient populations, some patients with type 2 diabetes taking WEGOVY tablets may experience subtherapeutic semaglutide blood concentrations. In patients with type 2 diabetes with an inadequate response to WEGOVY tablets, consider alternative therapies, including switching to WEGOVY injection [see Dosage and Administration (2.5)].

10 OVERDOSAGE

Overdoses have been reported with other GLP-1 receptor agonists. Effects have included severe nausea, severe vomiting, and severe hypoglycemia. In the event of overdose, appropriate supportive treatment should be initiated according to the patient’s clinical signs and symptoms. In the event of an overdose of WEGOVY, consider contacting the Poison Help line (1-800-222-1222) or a medical toxicologist for additional overdosage management recommendations. A prolonged period of observation and treatment for these symptoms may be necessary, taking into account the long half-life of WEGOVY of approximately 1 week.

11 DESCRIPTION

WEGOVY contains semaglutide, a human GLP-1 receptor agonist (or GLP-1 analog). The peptide backbone is produced by yeast fermentation. The main protraction mechanism of semaglutide is albumin binding, facilitated by modification of position 26 lysine with a hydrophilic spacer and a C18 fatty di-acid. Furthermore, semaglutide is modified in position 8 to provide stabilization against degradation by the enzyme dipeptidyl-peptidase 4 (DPP-4). A minor modification was made in position 34 to ensure the attachment of only one fatty di-acid. The molecular formula is C187H291N45O59 and the molecular weight is 4113.58 g/mol.

Figure 1. Structural Formula of Semaglutide

WEGOVY injection is a sterile, aqueous, clear, colorless solution. Each 0.5 mL single-dose pen contains a solution of WEGOVY containing 0.25 mg, 0.5 mg or 1 mg of semaglutide; and each 0.75 mL single-dose pen contains a solution of WEGOVY containing 1.7 or 2.4 mg of semaglutide. Each 1 mL of WEGOVY contains the following inactive ingredients: disodium phosphate dihydrate, 1.42 mg; sodium chloride, 8.25 mg; and water for injection. WEGOVY has a pH of approximately 7.4. Hydrochloric acid or sodium hydroxide may be added to adjust pH.

WEGOVY tablets include semaglutide as a white to almost white hygroscopic powder. Each tablet of WEGOVY contains 1.5 mg, 4 mg, 9 mg or 25 mg of semaglutide and the following inactive ingredients: Salcaprozate sodium (SNAC) and magnesium stearate.

12 CLINICAL PHARMACOLOGY

12.1 Mechanism of Action

Semaglutide is a GLP-1 analogue with 94% sequence homology to human GLP-1. Semaglutide acts as a GLP-1 receptor agonist that selectively binds to and activates the GLP-1 receptor, the target for native GLP-1.

GLP-1 is a physiological regulator of appetite and caloric intake, and the GLP-1 receptor is present in several areas of the brain involved in appetite regulation. Animal studies show that semaglutide distributed to and activated neurons in brain regions involved in regulation of food intake.

The exact mechanism of semaglutide in CV risk reduction in adults has not been established.

For treatment of MASH in humans, the precise mechanism of action of semaglutide is not fully understood and may involve multiple pathways mediated by weight loss and other factors. In a mouse model of diet-induced MASH, treatment with semaglutide resulted in histological improvements in steatosis, inflammation, and fibrosis in liver compared to baseline, which was associated with body weight loss, intermittent periods of reduced food intake, and improvements in relevant biomarkers. The relationship between the pathophysiology of MASH in animal models and humans has not been fully established.

12.2 Pharmacodynamics

Semaglutide lowers body weight with greater fat mass loss than lean mass loss. Semaglutide decreases calorie intake. The effects are likely mediated by affecting appetite.

Semaglutide stimulates insulin secretion and reduces glucagon secretion in a glucose-dependent manner. These effects can lead to a reduction of blood glucose.

Gastric Emptying

Semaglutide delays gastric emptying.

Cardiac Electrophysiology (QTc)

The effect of semaglutide on cardiac repolarization was tested in a thorough QTc trial. Semaglutide did not prolong QTc intervals at subcutaneous doses up to 1.5 mg at steady state.

Noninvasive Liver Disease Markers

Semaglutide decreases liver fat content measured by Magnetic Resonance Imaging Proton Density Fat Fraction (MRI-PDFF), liver stiffness assessed by transient elastography (TE), Enhanced Liver Fibrosis (ELF) score, and the levels of the pro-peptide of type III collagen biomarker (Pro-C3). The clinical relevance of these changes is yet to be confirmed.

12.3 Pharmacokinetics

Absorption

WEGOVY Injection

Absolute bioavailability of semaglutide is 89% following subcutaneous administration. Maximum concentration of semaglutide is reached 1 to 3 days post dose.

Similar exposure was achieved with subcutaneous administration of semaglutide in the abdomen, thigh, or upper arm.

The average semaglutide steady state concentration following subcutaneous administration of WEGOVY 2.4 mg once weekly was approximately 75 nmol/L in patients with obesity or overweight (BMI greater than or equal to 27 kg/m^2). The steady state exposure concentrations increased proportionally with doses up to 2.4 mg once weekly.

WEGOVY Tablets

WEGOVY tablets are co-formulated with SNAC which facilitates the absorption of semaglutide after oral WEGOVY tablet administration. The absorption of semaglutide predominantly occurs in the stomach.

Absolute bioavailability of semaglutide is estimated to be approximately 1% to 2% following oral tablet administration. Maximum concentration of semaglutide is reached 1 hour post dose.

The average semaglutide steady state concentration following 25 mg tablet oral administration was approximately 77 nmol/L in patients with obesity or overweight (BMI greater than or equal to 27 kg/m^2). The steady-state concentrations increased approximately proportionally with doses up to 25 mg once daily.

In patients with overweight or obesity without type 2 diabetes, semaglutide concentrations following once-daily administration of oral WEGOVY 25 mg tablet are predicted to be comparable to WEGOVY 2.4 mg once-weekly injection, with higher variability in semaglutide concentrations compared to subcutaneous administration (90% of patients had average concentrations between 27 and 186 nmol/L with WEGOVY 25 mg tablet versus 51 and 110 nmol/L with WEGOVY 2.4 mg once-weekly injection).

Effect of Volume and Timing of Water Consumption: Single doses of oral semaglutide tablet were administered with 50 mL or 240 mL of water after an 8-hour overnight fast and a continued fast of 4 hours post-dose in healthy subjects. Semaglutide absorption [i.e., area under the curve (AUC) and peak concentrations (Cmax)] was higher following dosing with 50 mL water compared to that of 240 mL water.

For 10 days, healthy subjects received once daily doses of oral semaglutide with 50 mL or 120 mL of water under fasting conditions with post-dose fasting period of 15, 30, 60, or 120 minutes. In this study, semaglutide absorption (i.e., AUC and Cmax) was higher after a longer post-dose fasting period. There were no clinically significant differences in semaglutide absorption with administration of 50 mL or 120 mL of water.

Distribution

The mean volume of distribution of semaglutide following subcutaneous administration in patients with obesity or overweight is approximately 12.5 L. Semaglutide is extensively bound to plasma albumin (greater than 99%) which results in decreased renal clearance and protection from degradation.

Elimination

The apparent clearance of semaglutide in patients with overweight or obesity is approximately 0.05 L/h. With an elimination half-life of approximately 1 week, semaglutide will be present in the circulation for about 5 to 7 weeks after the last injectable dose of 2.4 mg or oral dose of 25 mg.

Metabolism

The primary route of elimination for semaglutide is metabolism following proteolytic cleavage of the peptide backbone and sequential beta-oxidation of the fatty acid sidechain.

Excretion

The primary excretion routes of semaglutide-related material are via the urine and feces. Approximately 3% of the dose is excreted in the urine as intact semaglutide.

Specific Populations

Age, Sex, Race, Ethnicity, Body Weight, and Other Intrinsic Factors

No clinically significant differences in semaglutide pharmacokinetics were observed based on age (<65 years, 65-74, ≥75 years old), sex, race (White, Asian, or Black or African American), ethnicity, body weight, upper GI disease (i.e. chronic gastritis and/or gastroesophageal reflux disease), renal impairment [estimated glomerular filtration rate (eGFR) ≥30 to <90 mL/minute], or mild, moderate, and severe hepatic impairment (Child-Pugh Class A-C) or fibrosis stage (F2 or F3 in patients with MASH).

There is no difference observed in the exposure of semaglutide following subcutaneous administration of WEGOVY between patients with MASH and patients with overweight or obesity.

Patients with Type 2 Diabetes:

The average semaglutide steady state concentration following subcutaneous administration of WEGOVY 2.4 mg once weekly was approximately 68 nmol/L in patients with type 2 diabetes and obesity or overweight (BMI greater than or equal to 27 kg/m^2). The average semaglutide steady state concentration following 25 mg oral administration was approximately 44 nmol/L in patients with type 2 diabetes and obesity or overweight (BMI greater than or equal to 25 kg/m^2) with higher variability in semaglutide concentrations compared to subcutaneous administration (90% of patients had average concentrations between 11 nmol/L and 134 nmol/L with WEGOVY 25 mg tablet versus 47 nmol/L and 99 nmol/L with WEGOVY 2.4 mg once-weekly injection) [see Use in Specific Populations (8.6)].

Drug Interactions Studies

Subcutaneous Injection

The delay of gastric emptying with semaglutide may influence the absorption of concomitantly administered oral medications [see Drug Interactions (7.2)].

Oral Tablets

Clinical Studies and Model-Informed Approaches: The delay of gastric emptying with semaglutide may influence the absorption of concomitantly administered oral drugs [see Drug Interactions (7.2)]. Trials were conducted to study the potential effect of semaglutide on the absorption of oral drugs taken with semaglutide tablets administered orally at steady-state exposure.

Levothyroxine: Total thyroxine (i.e., adjusted for endogenous levels) AUC of was increased by 33% following administration of a single dose of levothyroxine 600 mcg concomitantly administered with oral semaglutide. Maximum exposure (Cmax) was unchanged.

Other Drugs: No clinically significant differences in semaglutide pharmacokinetics were observed when used concomitantly with omeprazole. No clinically significant differences in the pharmacokinetics of the following drugs were observed when used concomitantly with semaglutide: lisinopril, S-warfarin, R-warfarin, metformin, digoxin, ethinyl estradiol, levonorgestrel, furosemide or rosuvastatin.

In Vitro Studies: Semaglutide has very low potential to inhibit or induce CYP enzymes, and to inhibit drug transporters.

12.6 Immunogenicity

The observed incidence of anti-drug antibodies is highly dependent on the sensitivity and specificity of the assay. Differences in assay methods preclude meaningful comparisons of the incidence of anti-drug antibodies in the studies described below with the incidence of anti-drug antibodies in other studies, including those of semaglutide or of other semaglutide products.

During the 68-week treatment periods in Studies 2 and 3 in adults [see Clinical Studies (14.2)], 50/1709 (3%) of WEGOVY injection-treated patients developed anti-semaglutide antibodies (referred to as anti-drug-antibodies or ADA). Of these 50 WEGOVY injection-treated patients, 28 patients (2% of the total WEGOVY injection-treated study population) developed antibodies that cross-reacted with native GLP-1. In adults with MASH treated with WEGOVY for 72 weeks in Study 9 [see Clinical Studies (14.4)], 3/763 (0.4%) of patients developed ADA which were also cross-reactive to native GLP-1. No identified clinically significant effect of ADA on pharmacokinetics for WEGOVY injection was observed. There is insufficient evidence to characterize the effects of ADA on pharmacodynamics, safety, or effectiveness of semaglutide products.

13 NONCLINICAL TOXICOLOGY

13.1 Carcinogenesis, Mutagenesis, Impairment of Fertility

In a 2-year carcinogenicity study in CD-1 mice, subcutaneous doses of 0.3, 1 and 3 mg/kg/day (2-, 8-, and 22-fold the maximum recommended human dose [MRHD] of WEGOVY subcutaneous injection 2.4 mg/week, or WEGOVY oral tablet 25 mg daily based on AUC) were administered to the males, and 0.1, 0.3 and 1 mg/kg/day (0.6-, 2-, and 5-fold MRHD) were administered to the females. A statistically significant increase in thyroid C-cell adenomas and a numerical increase in C-cell carcinomas were observed in males and females at all dose levels (greater than or equal to 0.6 times human exposure).

In a 2-year carcinogenicity study in Sprague Dawley rats, subcutaneous doses of 0.0025, 0.01, 0.025 and 0.1 mg/kg/day were administered (below quantification, 0.2-, 0.4-, and 2-fold the exposure at the MRHD). A statistically significant increase in thyroid C-cell adenomas was observed in males and females at all dose levels, and a statistically significant increase in thyroid C-cell carcinomas was observed in males at greater than or equal to 0.01 mg/kg/day, at clinically relevant exposures.

Human relevance of thyroid C-cell tumors in rats is unknown and could not be determined by clinical studies or nonclinical studies [see Boxed Warning, Warnings and Precautions (5.1)]. Semaglutide was not mutagenic or clastogenic in a standard battery of genotoxicity tests (bacterial mutagenicity [Ames] human lymphocyte chromosome aberration, rat bone marrow micronucleus).

In a combined fertility and embryo-fetal development study in rats, subcutaneous doses of 0.01, 0.03 and 0.09 mg/kg/day (0.04-, 0.1-, and 0.4-fold the MRHD) were administered to male and female rats. Males were dosed for 4 weeks prior to mating, and females were dosed for 2 weeks prior to mating and throughout organogenesis until Gestation Day 17. No effects were observed on male fertility. In females, an increase in estrus-cycle length was observed at all dose levels, together with a small reduction in numbers of corpora lutea at greater than or equal to 0.03 mg/kg/day. These effects were likely an adaptive response secondary to the pharmacological effect of semaglutide on food consumption and body weight.

13.2 Animal Toxicology and/or Pharmacology

The WEGOVY tablet contains SNAC as an absorption enhancer. An increase in lactate levels and a decrease in glucose levels in the plasma and cerebrospinal fluid (CSF) were observed in mechanistic studies with SNAC in rats. Small but statistically significant increases in lactate levels (up to 2-fold) were observed in a few animals at approximately the clinical exposure. At higher exposures these findings were associated with moderate to marked adverse clinical signs (lethargy, abnormal respiration, ataxia, and reduced activity, body tone and reflexes) and marked decreases in plasma and CSF glucose levels. These findings are consistent with inhibition of cellular respiration and lead to mortality at SNAC concentrations >100-times the clinical Cmax.

14 CLINICAL STUDIES

14.1 Cardiovascular Outcomes Trial in Adult Patients with Cardiovascular Disease and Either Obesity or Overweight

Overview of Clinical Trial

Study 1 (NCT03574597) was a multi-national, multi-center, placebo-controlled, double-blind trial to determine the effect of WEGOVY injection relative to placebo on major adverse CV events (MACE) when added to current standard of care, which included management of CV risk factors and individualized healthy lifestyle counseling (including diet and physical activity) in adults with established CV disease and either obesity or overweight. The primary endpoint, MACE, was the time to first occurrence of a three-part composite outcome which included CV death, non-fatal myocardial infarction, and non-fatal stroke. During the 16-week dose escalation period, patients were titrated to WEGOVY 2.4 mg injected subcutaneously once weekly or placebo. Patients who could not tolerate the recommended escalation dosage, could stay at a lower dose level.

All patients were 45 years or older, with an initial BMI of 27 kg/m^2 or greater and established CV disease (prior myocardial infarction, prior stroke, or peripheral arterial disease). Patients with a history of type 1 or type 2 diabetes were excluded. Concomitant CV therapies could be adjusted, at the discretion of the investigator, to ensure participants were treated according to the current standard of care for patients with established CV disease.

In this trial, 17,604 patients were randomized to WEGOVY injection or placebo. At baseline, the mean age was 62 years (range 45-93), 72% were male, 84% were White, 4% were Black or African American, and 8% were Asian, and 10% were Hispanic or Latino. Mean baseline body weight was 97 kg and mean BMI was 33 kg/m^2. At baseline, prior myocardial infarction was reported in 76% of randomized individuals, prior stroke in 23%, and peripheral arterial disease in 9%. Heart failure was reported in 24% of patients. At baseline, CV disease and risk factors were managed with lipid-lowering therapy (90%), platelet aggregation inhibitors (86%), angiotensin converting enzyme inhibitors or angiotensin II receptor blockers (74%), and beta blockers (70%). A total of 10% had moderate renal impairment (eGFR 30 to <60 mL/min/1.73m^2) and 0.4% had severe renal impairment eGFR <30 mL/min/1.73m^2.

Results

In total, 96.9% of patients completed the trial, and vital status was available for 99.4% of patients. The median follow-up duration was 41.8 months. A total of 31% of WEGOVY injection-treated patients and 27% of placebo-treated patients permanently discontinued study drug. Of those patients on treatment at 1 year, 76% were on the 2.4 mg dose, 8% were on the 1.7 mg dose, and 16% were on lower doses. Of those patients on treatment at 2 years, 77% were on the 2.4 mg dose, 7% were on the 1.7 mg dose, and 17% were on lower doses.

For the primary analysis, a Cox proportional hazards model was used to test for superiority. Type 1 error was controlled across multiple tests.

WEGOVY injection significantly reduced the risk for first occurrence of MACE. The estimated hazard ratio (95% CI) was 0.80 (0.72, 0.90) (see Figure 2 and Table 5).

Figure 2. Cumulative Incidence Function: Time to First Occurrence of MACE in Study 1 with WEGOVY Injection

Data from the in-trial period. Cumulative incidence estimates are based on time from randomization to first EAC-confirmed cardiovascular death, non-fatal myocardial infarction, or non-fatal stroke with non-CV death modeled as competing risk using the Aalen-Johansen estimator. Patients without events of interest were censored at the end of their in-trial observation period. Time from randomization to first cardiovascular death, non-fatal myocardial infarction, or non-fatal stroke was analyzed using a Cox proportional hazards model with treatment as categorical fixed factor. The hazard ratio and confidence interval are adjusted for the group sequential design using the likelihood ratio ordering.

HR: Hazard ratio; CI: confidence interval; CV: cardiovascular

The treatment effect for the primary composite endpoint, its components, and other relevant endpoints in Study 1 are shown in Table 5.

Table 5. Treatment Effect for MACE and Other Events in Study 1 with WEGOVY Injection

 | Patients with events n (%)
 | Placebo N=8,801 | WEGOVY Injection N=8,803 | Hazard Ratio (95% CI)
Primary composite endpoint
Composite of CV death, non-fatal myocardial infarction, or non-fatal stroke^1 | 701 (8%) | 569 (6.5%) | 0.8 (0.72; 0.9)*^2
Key secondary endpoints
CV death^3 | 262 (3%) | 223 (2.5%) | 0.85 (0.71; 1.01)
All-cause death^4 | 458 (5.2%) | 375 (4.3%) | 0.81 (0.71; 0.93)
Other endpoints
Fatal or non-fatal myocardial infarction^5 | 334 (3.8%) | 243 (2.8%) | 0.72 (0.61; 0.85)
Fatal or non-fatal stroke^5 | 178 (2%) | 160 (1.8%) | 0.89 (0.72; 1.11)
Hospitalization for heart failure or urgent heart failure visits^5,6 | 122 (1.4%) | 97 (1.1%) | 0.79 (0.60; 1.03)

* p-value <0.001, one-sided p-value

^1 Primary endpoint

^2 Adjusted for group sequential design using the likelihood ratio ordering.

^3 CV death was the first confirmatory secondary endpoint in the testing hierarchy and superiority was not confirmed.

^4 Confirmatory secondary endpoint. Not statistically significant based on the prespecified testing hierarchy.

^5 Not included in the prespecified testing hierarchy for controlling type-I error.

^6 Effect on heart failure has not been established.

NOTE: Time to first event was analyzed in a Cox proportional hazards model with treatment as factor. For patients with multiple events, only the first event contributed to the composite endpoint.

Table 6. Mean Changes in Anthropometry and Cardiometabolic Parameters at Week 104 in Study 1^1,2

 |  | PLACEBO |  | WEGOVY Injection
 |  | Baseline | Change from Baseline (LSMean) | Baseline | Change from Baseline (LSMean) | Difference from Placebo (LSMean)
Body Weight (kg) |  | 96.8 | -0.9^3 | 96.5 | -9.4^3 | -8.5^3
Waist Circumference (cm) |  | 111.4 | -1 | 111.3 | -7.6 | -6.5
Systolic Blood Pressure (mmHg) |  | 131 | -0.5 | 131 | -3.8 | -3.3
Diastolic Blood Pressure (mmHg) |  | 79 | -0.5 | 79 | -1 | -0.5
Heart Rate |  | 69 | 0.7 | 69 | 3.8 | 3.1
HbA1c (%) |  | 5.8 | 0 | 5.8 | -0.3 | -0.3
 | Baseline |  | % Change from Baseline (LSMean) | Baseline | % Change from Baseline (LSMean) | Relative difference from placebo (%) (LSMean)
Total Cholesterol (mg/dL)^4 | 156 |  | -1.9 | 155.5 | -4.6 | -2.8
LDL Cholesterol (mg/dL)^4 | 78.5 |  | -3.1 | 78.5 | -5.3 | -2.2
HDL Cholesterol (mg/dL)^4 | 44.2 |  | 0.6 | 44.1 | 4.9 | 4.2
Triglycerides (mg/dL)^4 | 139.5 |  | -3.2 | 138.6 | -18.3 | -15.6

^1 Parameters listed in the table were not included in the pre-specified hierarchical testing.

^2 Responses were analyzed using an ANCOVA with treatment as fixed factor and baseline value as covariate. Before analysis, missing data were multiple imputed. The imputation model (linear regression) was done separately for each treatment arm and included baseline value as a covariate and was fitted to all subjects with a measurement regardless of treatment status at Week 104.

^3 For body weight the ‘change from baseline’ and ‘difference to placebo’ the unit is percentage change from baseline.

^4 Baseline value is the geometric mean.

The reduction of MACE with WEGOVY injection was not impacted by age, sex, race, ethnicity, BMI at baseline, or level of renal function impairment.

14.2 Weight Reduction and Long-term Maintenance Studies in Adults with Obesity or Overweight

Overview of Clinical Studies in Adults

The efficacy of WEGOVY once weekly subcutaneous injection for weight reduction and long-term maintenance of body weight in conjunction with a reduced-calorie diet and increased physical activity were studied in three 68-week, randomized, double-blind, placebo-controlled trials; one 68-week, randomized, double-blind, placebo withdrawal trial; one 68-week, randomized, double-blind trial that investigated 2 different doses of WEGOVY injection versus placebo. In Studies 2 (NCT#03548935), 3 (NCT#03552757), and 4 (NCT#03611582), WEGOVY or matching placebo was escalated to 2.4 mg subcutaneous injection weekly during a 16-week period followed by 52 weeks on maintenance dose. In Study 5 (NCT#03548987), WEGOVY injection was escalated during a 20-week run-in period, and patients who reached a WEGOVY 2.4 mg subcutaneous injection weekly dosage after the run-in period were randomized to either continued treatment with WEGOVY injection or placebo for 48 weeks. In Study 6 (NCT#03811574), WEGOVY injection was escalated to 1.7 mg or 2.4 mg subcutaneous weekly dosages or placebo over 12 to 16 weeks followed by 52 weeks on either maintenance dose.

The efficacy of WEGOVY 25 mg oral once daily tablet for weight reduction and long-term maintenance of body weight in conjunction with a reduced-calorie diet and increased physical activity was evaluated in a 64-week randomized, double-blind, placebo-controlled trial [Study 7 (NCT#05564117)]. WEGOVY tablet or matching placebo was escalated to a 25 mg tablet once daily during a 12-week period followed by 52-week maintenance period.

In Studies 2, 3, 5 and 7, all patients received instruction for a reduced-calorie diet (approximately 500 kcal/day deficit) and increased physical activity counseling (recommended to a minimum of 150 min/week) that began with the first dose of study medication or placebo and continued throughout the trial. In Study 4, patients received an initial 8-week low-calorie diet (total energy intake 1,000 to 1,200 kcal/day) followed by 60 weeks of a reduced-calorie diet (1200 to 1800 kcal/day) and increased physical activity (100 mins/week with gradual increase to 200 mins/week).

Study 2 was a 68-week trial that enrolled 1,961 patients with obesity (BMI greater than or equal to 30 kg/m^2) or with overweight (BMI 27 to 29.9 kg/m^2) and at least one weight-related comorbid condition, such as treated or untreated dyslipidemia or hypertension; patients with type 2 diabetes mellitus were excluded. Patients were randomized in a 2:1 ratio to either WEGOVY injection or placebo. At baseline, mean age was 46 years (range 18 to 86), 74% were female, 75% were White, 13% were Asian and 6% were Black or African American. A total of 12% were Hispanic or Latino ethnicity. Mean baseline body weight was 105.3 kg and mean BMI was 37.9 kg/m^2.

Study 3 was a 68-week trial that enrolled 807 patients with type 2 diabetes and BMI greater than or equal to 27 kg/m^2. Patients included in the trial had HbA1c 7-10% and were treated with either: diet and exercise alone or 1 to 3 oral anti‑diabetic drugs (metformin, sulfonylurea, glitazone or sodium-glucose co-transporter 2 inhibitor). Patients were randomized in a 1:1 ratio to receive either WEGOVY injection or placebo. At baseline, the mean age was 55 years (range 19 to 84), 51% were female, 62% were White, 26% were Asian and 8% were Black or African American. A total of 13% were Hispanic or Latino ethnicity. Mean baseline body weight was 99.8 kg and mean BMI was 35.7 kg/m^2.

Study 4 was a 68-week trial that enrolled 611 patients with obesity (BMI greater than or equal to 30 kg/m^2) or with overweight (BMI 27 to 29.9 kg/m^2) and at least one weight-related comorbid condition such as treated or untreated dyslipidemia or hypertension; patients with type 2 diabetes mellitus were excluded. The patients were randomized in a 2:1 ratio to receive either WEGOVY injection or placebo. At baseline, the mean age was 46 years, 81% were female, 76% were White, 19% were Black or African American and 2% were Asian. A total of 20% were Hispanic or Latino ethnicity. Mean baseline body weight was 105.8 kg and mean BMI was 38 kg/m^2.

Study 5 was a 68-week trial that enrolled 902 patients with obesity (BMI greater than or equal to 30 kg/m^2) or with overweight (BMI 27 to 29.9 kg/m^2) and at least one weight-related comorbid condition such as treated or untreated dyslipidemia or hypertension; patients with type 2 diabetes mellitus were excluded. Mean body weight at baseline for the 902 patients was 106.8 kg and mean BMI was 38.3 kg/m². All patients received WEGOVY injection during the run-in period of 20 weeks that included 16 weeks of dose escalation. Trial product was permanently discontinued before randomization in 99 of 902 patients (11%); the most common reason was adverse reactions (n=48, 5.3%); 803 patients reached WEGOVY 2.4 mg injection and were then randomized in a 2:1 ratio to either continue on WEGOVY injection or receive placebo. Among the 803 randomized patients, the mean age was 46 years, 79% were female, 84% were White, 13% were Black or African American, and 2% Asian. A total of 8% were Hispanic or Latino ethnicity. Mean body weight at randomization (Week 20) was 96.1 kg and mean BMI at randomization (Week 20) was 34.4 kg/m^2.

Study 6 was a 68-week trial that enrolled 401 East-Asian patients (Japan and South Korea) with BMI greater than or equal to 35 kg/m^2 and at least one weight-related comorbid condition or with BMI 27 to 34.9 kg/m^2 and at least two weight-related comorbid conditions. The patients were randomized 2:1:1 to receive subcutaneous injection of WEGOVY 2.4 mg, WEGOVY 1.7 mg, or placebo. At baseline, the mean age was 51 years, 63% were male, and all patients were Asian. Mean baseline body weight was 87.5 kg and mean BMI was 31.9 kg/m^2. At baseline, 24.7% of patients had type 2 diabetes mellitus.

Study 7 was a 64-week trial that enrolled 307 patients with obesity (BMI greater than or equal to 30 kg/m^2) or with overweight (BMI 27-29.9 kg/m^2) and at least one weight-related comorbid condition, such as treated or untreated dyslipidemia or hypertension; patients with type 2 diabetes mellitus were excluded. Patients were randomized in a 2:1 ratio to either WEGOVY 25 mg tablet or placebo. At baseline, mean age was 48 years, 79% were women, 92% were White, 1% were Asian and 7% were Black or African American. A total of 7.8% were Hispanic or Latino ethnicity. Mean baseline body weight was 106 kg and mean BMI was 38 kg/m^2.

Results

In Studies 2, 3, and 4, 16% of WEGOVY injection-treated patients and 19% of the placebo-treated patients discontinued therapy. In these studies, 6.8% of WEGOVY injection-treated patients and 3.2% of placebo-treated patients discontinued their treatment due to an adverse reaction [see Adverse Reactions (6.1)]. In Study 5, the proportions of patients who discontinued study drug were 5.8% and 11.6% for WEGOVY injection and placebo, respectively. In Study 6, the proportions of patients who discontinued study drug were 7.9%, 6.5%, and 3% for WEGOVY 1.7 mg injection, WEGOVY 2.4 mg injection, and placebo, respectively. In Study 7, the proportions of patients who discontinued study drug were 18% and 25.5% for WEGOVY 25 mg tablet and placebo, respectively. Adverse reactions led to treatment discontinuation in 6.8% of patients treated with WEGOVY 25 mg tablet and 5.9% patients receiving placebo.

For Studies 2, 3 and 4, the primary efficacy parameters were mean percent change in body weight and the percentages of patients achieving greater than or equal to 5% weight loss from baseline to Week 68.

After 68 weeks, treatment with WEGOVY injection resulted in a statistically significant reduction in body weight compared with placebo. Greater proportions of patients treated with WEGOVY injection achieved 5%, 10% and 15% weight loss than those treated with placebo as shown in Table 7.

Table 7. Changes in Body Weight at Week 68 in Studies 2, 3, and 4 with WEGOVY Injection

 | Study 2 (Obesity or overweight with comorbidity) |  | Study 3 (Type 2 diabetes with obesity or overweight) |  | Study 4 (Obesity or overweight with comorbidity undergoing intensive lifestyle therapy)
Intention-to-Treat^1 | PLACEBO N=655 | WEGOVY Injection N=1,306 | PLACEBO N=403 | WEGOVY Injection N=404 | PLACEBO N=204 | WEGOVY Injection N=407
Body Weight
Baseline mean (kg) | 105.2 | 105.4 | 100.5 | 99.9 | 103.7 | 106.9
% change from baseline (LSMean) | -2.4 | -14.9 | -3.4 | -9.6 | -5.7 | -16
% difference from placebo (LSMean) (95% CI) |  | -12.4 (‑13.3; ‑11.6)* |  | -6.2 (-7.3; -5.2)* |  | -10.3 (-11.8; -8.7)*
% of Patients losing greater than or equal to 5% body weight | 31.1 | 83.5 | 30.2 | 67.4 | 47.8 | 84.8
% difference from placebo (LSMean) (95% CI) |  | 52.4; (48.1; 56.7)* |  | 37.2 (30.7; 43.8)* |  | 37 (28.9; 45.2)*
% of Patients losing greater than or equal to 10% body weight | 12 | 66.1 | 10.2 | 44.5 | 27.1 | 73
% difference from placebo (LSMean) (95% CI) |  | 54.1; (50.4; 57.9)* |  | 34.3 (28.4; 40.2)* |  | 45.9; (38; 53.7)*
% of Patients losing greater than or equal to 15% body weight | 4.8 | 47.9 | 4.3 | 25.1 | 13.2 | 53.4
% difference from placebo (LSMean) (95% CI) |  | 43.1; (39.8; 46.3)* |  | 20.7; (15.7; 25.8)* |  | 40.2 (33.1; 47.3)*
% of Patients losing greater than or equal to 20% body weight^2 | 1.7 | 30.2 | 2.3 | 12.8 | 3.5 | 33.9
% difference from placebo (LSMean) (95% CI)^2 |  | 28.6 (25,8; 31.3) |  | 10.6; (6.4; 14.7) |  | 30.4; (24.8; 36.1)

LSMean = least squares mean; CI = confidence interval

^1 The intent-to-treat population includes all randomized patients. In Study 2, at Week 68, the body weight was missing for 7.2% and 11.9% of patients randomized to WEGOVY injection and placebo, respectively. In Study 3, at Week 68, the body weight was missing for 4% and 6.7% of patients randomized to WEGOVY injection and placebo, respectively. In Study 4, at Week 68, the body weight was missing for 8.4% and 7.4% of patients randomized to WEGOVY injection and placebo, respectively. Missing data were imputed from retrieved subjects of the same randomized treatment arm (RD-MI).

^2 Not included in the pre-specified hierarchical testing.

* p<0.0001 (unadjusted 2-sided) for superiority.

For Study 5, the primary efficacy parameter was mean percent change in body weight from randomization (Week 20) to Week 68.

From randomization (week 20) to Week 68, treatment with WEGOVY injection resulted in a statistically significant reduction in body weight compared with placebo (Table 8). Because patients who discontinued WEGOVY injection during titration and those who did not reach the 2.4 mg weekly dose were not eligible for the randomized-treatment period, the results may not reflect the experience of patients in the general population who are first starting WEGOVY injection.

Table 8. Changes in Body Weight at Week 68 in Study 5 (Obesity or Overweight with Comorbidity After 20-week Run-in) with WEGOVY Injection

 | WEGOVY Injection; N=803^1
Body Weight (only randomized patients)
Mean at Week 0 (kg) | 107.2
 | PLACEBO; N=268 | WEGOVY Injection; N=535
Body Weight
Mean at Week 20 (SD) (kg) | 95.4 (22.7) | 96.5 (22.5)
% change from Week 20 at Week 68 (LSMean) | 6.9 | -7.9
% difference from placebo (LSMean) (95% CI) |  | -14.8 (-16; -13.5)*

LSMean = least squares mean; CI = confidence interval

^1 902 patients were enrolled at Week 0 with a mean baseline body weight of 106.8 kg. The intent-to-treat population includes all randomized patients. At Week 68, the body weight was missing for 2.8% and 6.7% of patients randomized to WEGOVY injection and placebo, respectively. Missing data were imputed from retrieved subjects of the same randomized treatment arm (RD-MI).

* p<0.001 (unadjusted 2-sided) for superiority, controlled for multiplicity.

For Study 6, the primary efficacy parameters were mean percent change in body weight and the percentage of patients achieving greater than or equal to 5% weight loss from baseline to Week 68.

After 68 weeks, treatment with WEGOVY 1.7 mg and 2.4 mg injection resulted in a statistically significant reduction in body weight compared with placebo. Greater proportions of patients treated with WEGOVY injection achieved 5%, 10%, and 15% weight loss than those treated with placebo as shown in Table 9.

Table 9. Changes in Body Weight at Week 68 in Study 6 in East-Asian Patients (WEGOVY 1.7 mg) with WEGOVY Injection

 | Study 6 (BMI ≥35 kg/m^2 with at least one comorbidity or; BMI 27-34.9 kg/m^2 with at least two comorbidities)
Intention-to-treat^1 | PLACEBO; N=101 | WEGOVY 1.7 mg Injection; N=101 | WEGOVY 2.4 mg Injection; N=199
Body Weight
Baseline mean (kg) | 90.2 | 86.1 | 86.9
% change from baseline (LSMean) | -2.1 | -9.6 | -13.2
% difference from placebo (LSMean) (95% CI) |  | -7.5; (-9.6; -5.4)* | -11.1; (-12.9; -9.2)*
% of Patients losing greater than or equal to 5% body weight | 19.4 | 72.8 | 84
% difference from placebo (LSMean) (95% CI) |  | 53.3; (41; 65.6)* | 64.5; (54.8; 74.3)*
% of Patients losing greater than or equal to 10% body weight | 4.5 | 39.1 | 59.9
% difference from placebo (LSMean) (95% CI) |  | 34.5; (23.9; 45.1)* | 55.4; (47.3; 63.6)*
% of Patients losing greater than or equal to 15% body weight | 2.6 | 20.8 | 38.2
% difference from placebo (LSMean) (95% CI) |  | 18.2; (9.8; 26.7)* | 35.6; (27.9; 43.3)*

LSMean = least squares mean; CI = confidence interval

^1 The intent-to-treat population includes all randomized patients. At baseline, 24.7% of patients had type 2 diabetes mellitus. At Week 68, the body weight was missing for 3%, 3%, and 1% of patients randomized to WEGOVY 1.7 mg injection, WEGOVY 2.4 mg injection, and placebo, respectively. Missing data were imputed from retrieved subjects of the same randomized treatment arm (RD-MI).

* p<0.0001 (unadjusted 2-sided) for superiority.

For Study 7, the primary efficacy parameters were mean percent change in body weight and the percentages of patients achieving greater than or equal to 5% weight loss from baseline to Week 64.

After 64 weeks, treatment with WEGOVY tablets resulted in a statistically significant reduction in body weight compared with placebo. Greater proportions of patients treated with WEGOVY tablets achieved 5%, 10%, 15% and 20% weight loss than those treated with placebo as shown in Table 10.

Table 10. Changes in Body Weight at Week 64 in Study 7 with WEGOVY Tablet

 | Study 7 (Obesity or overweight with comorbidity)
Intention-to-Treat^1 | PLACEBO N = 102 | WEGOVY Tablet N = 205
Body Weight
Baseline mean (kg) | 104.8 | 106.4
% change from baseline (LSMean)^3 | -2.4 | -13.6
% difference from placebo (LSMean) (95% CI)^3 |  | -11.2 [-13.6; -8.8]^2
% of Patients losing greater than or equal to 5% body weight^3 | 31.3 | 76.3
% difference from placebo (LSMean) (95% CI)^3 |  | 45.1 [33.8; 56.3]^2
% of Patients losing greater than or equal to 10% body weight | 14.4 | 59.8
% difference from placebo (LSMean) (95% CI)^3 |  | 45.3 [35.5; 55.2]^2
% of Patients losing greater than or equal to 15% body weight^3 | 5.5 | 47.0
% difference from placebo (LSMean) (95% CI)^3 |  | 41.5 [33.2; 49.8]^2
% of Patients losing greater than or equal to 20% body weight^3 | 3.1 | 27.9
% difference from placebo (LSMean) (95% CI)^3 |  | 24.8 [17.7; 31.9]^2

LSMean = least squares mean; CI = confidence interval

^1 The intent-to-treat population includes all randomized patients. In Study 7, at Week 64, the body weight was missing for 6.3% and 11.8% of patients randomized to WEGOVY tablets and placebo, respectively.

^2 p<0.0001 (unadjusted 2-sided) for superiority.

^3 Model based estimates are based on an analysis of covariance (or logistic regression for the 5%, 10%, 15% or 20% achievement endpoints) including treatment as a factor and baseline value as a covariate. Missing data were multiple imputed from retrieved subjects of the same randomized treatment arm (RD-MI). The imputation model was a linear regression of the endpoint with gender as factor and baseline value of the endpoint, timing and the value of last available observation – on study (LAO-OS) of the endpoint as covariates, imputed by treatment status. For the 5%, 10%, 15% or 20% achievement endpoints, the missing body weight measurements were imputed before performing the logistic regression analyses.

RD-MI: Retrieved Drop-outs Multiple Imputation

A reduction in body weight was observed with WEGOVY irrespective of age, sex, race, ethnicity, BMI at baseline, body weight (kg) at baseline, and level of renal function impairment.

The cumulative frequency distributions of change in body weight are shown in Figure 3, Figure 4 and Figure 5 for Studies 2, 3 and 7. One way to interpret this figure is to select a change in body weight of interest on the horizontal axis and note the corresponding proportions of patients (vertical axis) in each treatment group who achieved at least that degree of weight loss. For example, note that the vertical line arising from ‑10% in Study 2 intersects the WEGOVY injection and placebo curves at approximately 66%, and 12%, respectively, which correspond to the values shown in Table 8.

Figure 3. Change in Body Weight (%) from Baseline to Week 68 (Study 2) with WEGOVY Injection

Observed data from in-trial period including imputed data for missing observations (RD-MI).

Figure 4. Change in Body Weight (%) from Baseline to Week 68 (Study 3) with WEGOVY Injection

Observed data from in-trial period including imputed data for missing observations (RD-MI).

Figure 5. Change in Body Weight (%) from Baseline to Week 64 (Study 7) with WEGOVY Tablets

Observed data from in-trial period including imputed data for missing observations (RD-MI). The missing observation was the patient-level average from the 1,000 imputed datasets.

The time courses of weight loss with WEGOVY injection and placebo from baseline through Week 68 are depicted in Figure 6, Figure 7 and Figure 8.

Figure 6. Change from Baseline (%) in Body Weight (Study 2 on Left and Study 3 on Right) with WEGOVY Injection

Observed values for patients completing each scheduled visit, and estimates with multiple imputations from retrieved dropouts (RD-MI).

Figure 7. Change from Baseline (%) in Body Weight (Study 4 on Left and Study 5a on Right) with WEGOVY Injection

Observed values for patients completing each scheduled visit, and estimates with multiple imputations from retrieved dropouts (RD-MI).

a Change from Week 0 was not a primary endpoint in Study 5. Dotted line indicates time of randomization. Randomized patients (shown) do not include 99 patients that discontinued during the 20-week run-in period.

Figure 8. Change in Body Weight (%) from Baseline to Week 68 (Study 6 in East-Asian Patients) with WEGOVY Injection

Observed values for patients completing each scheduled visit and estimates with multiple imputations from retrieved dropouts (RD-MI). At baseline, 24.7% of patients had type 2 diabetes mellitus.

Effect of WEGOVY Injection on Anthropometry and Cardiometabolic Parameters in Adults

Changes in waist circumference and cardiometabolic parameters with WEGOVY injection are shown in Table 11 for Studies 2, 3, and 4; in Table 12 for Study 5; and in Table 13 for Study 6.

Table 11. Changes in Anthropometry and Cardiometabolic Parameters at Week 68 in Studies 2, 3 and 4 with WEGOVY Injection

 | Study 2 (Obesity or overweight with comorbidity) |  | Study 3 (Type 2 diabetes with obesity or overweight) |  | Study 4 (Obesity or overweight with comorbidity undergoing intensive lifestyle therapy)
Intention-to-Treat | PLACEBO N=655 | WEGOVY Injection N=1,306 | PLACEBO N=403 | WEGOVY Injection N=404 | PLACEBO N=204 | WEGOVY Injection N=407
Waist Circumference (cm); Baseline Changes from baseline (LSMean^1) Difference from placebo (LSMean) | 114.8; -4.1 | 114.6; -13.5; -9.4 | 115.5; -4.5 | 114.5; -9.4; -4.9 | 111.8; -6.3 | 113.6; -14.6; -8.3
Systolic Blood Pressure (mmHg); Baseline Changes from baseline (LSMean^1) Difference from placebo (LSMean) | 127; -1.1 | 126; -6.2; -5.1 | 130; -0.5 | 130; -3.9; -3.4 | 124; -1.6 | 124; -5.6; -3.9
Diastolic Blood Pressure (mmHg)^2; Baseline Changes from baseline (LSMean^1) Difference from placebo (LSMean) | 80; -0.4 | 80; -2.8; -2.4 | 80; -0.9 | 80; -1.6; -0.7 | 81; -0.8 | 80; -3; -2.2
Heart Rate^2,3; Baseline Changes from baseline (LSMean^1) Difference from placebo (LSMean) | 72; -0.7 | 72; 3.5; 4.3 | 76; -0.2 | 75; 2.5; 2.7 | 71; 2.1 | 71; 3.1; 1
HbA1c (%)^2; Baseline Changes from baseline (LSMean^1) Difference from placebo (LSMean) | 5.7; -0.2 | 5.7; -0.4; -0.3 | 8.1; -0.4 | 8.1; -1.6; -1.2 | 5.8; -0.3 | 5.7; -0.5; -0.2
Total Cholesterol (mg/dL)^2,4; Baseline Percent Change from baseline (LSMean^1) Relative difference from placebo (LSMean) | 192.1; 0.1 | 189.6; -3.3; -3.3 | 170.8; -0.5 | 170.8; -1.4; -0.9 | 188.7; 2.1 | 185.4; -3.9; -5.8
LDL Cholesterol (mg/dL)^2,4; Baseline Percent Change from baseline (LSMean^1) Relative difference from placebo (LSMean) | 112.5; 1.3 | 110.3; -2.5; -3.8 | 90.1; 0.1 | 90.1; 0.5; 0.4 | 111.8; 2.6 | 107.7; -4.7; -7.1
HDL (mg/dL)^2,4; Baseline Percent Change from baseline (LSMean^1) Relative difference from placebo (LSMean) | 49.5; 1.4 | 49.4; 5.2; 3.8 | 43.8; 4.1 | 44.7; 6.9; 2.7 | 50.9; 5 | 51.6; 6.5; 1.5
Triglycerides (mg/dL)^2,4; Baseline Percent Change from baseline (LSMean^1) Relative difference from placebo (LSMean) | 127.9; -7.3 | 126.2; -21.9; -15.8 | 159.5; -9.4 | 154.9; -22; -13.9 | 110.9; -6.5 | 107.9; -22.5; -17

Missing data were imputed from retrieved subjects of the same randomized treatment arm (RD-MI)

^1 Model based estimates based on an analysis of covariance model including treatment (and stratification factors for Study 3 only) as a factor and baseline value as a covariate

^2 Not included in the pre-specified hierarchical testing (except HbA1c for Study 3)

^3 Model based estimates based on a mixed model for repeated measures including treatment (and stratification factors for Study 3 only) as a factor and baseline values as a covariate

^4 Baseline value is the geometric mean

Table 12. Mean Changes in Anthropometry and Cardiometabolic Parameters in Study 5 (Obesity or Overweight with Comorbidity After 20-week Run-in)^1 with WEGOVY Injection

 | PLACEBO; N=268 |  | WEGOVY Injection; N=535
 | Randomization; (Week 20) | Change from; Randomization; (Week 20) to; Week 68; (LSMean^1) | Randomization; (Week 20) | Change from; Randomization; (Week 20) to; Week 68; (LSMean^1) | Difference; from placebo; (LSMean)
Waist Circumference (cm) | 104.7 | 3.3 | 105.5 | -6.4 | -9.7
Systolic Blood Pressure (mmHg) | 121 | 4.4 | 121 | 0.5 | -3.9
Diastolic Blood Pressure (mmHg)^2 | 78 | 0.9 | 78 | 0.3 | -0.5
Heart Rate^2,3 | 76 | -5.3 | 76 | -2 | 3.3
HbA1c (%)^2 | 5.4 | 0.1 | 5.4 | -0.1 | -0.2
 | Randomization; (Week 20) | % Change; from; Randomization; (Week 20); (LSMean^1) | Randomization; (Week 20) | % Change; from; Randomization; (Week 20); (LSMean^1) | Relative; difference from; placebo; (LSMean)
Total Cholesterol (mg/dL)^2,4 | 175.1 | 11.4 | 175.9 | 4.9 | -5.8
LDL Cholesterol (mg/dL)^2,4 | 109.1 | 7.6 | 108.7 | 1.1 | -6.1
HDL Cholesterol (mg/dL)^2,4 | 43.6 | 17.8 | 44.5 | 18.2 | 0.3
Triglycerides (mg/dL)^2,4 | 95.3 | 14.8 | 98.1 | -5.6 | -17.8

Missing data were imputed from retrieved subjects of the same randomized treatment arm (RD-MI).

^1 Model based estimates based on an analysis of covariance model including treatment as a factor and baseline value as a covariate.

^2 Not included in the pre-specified hierarchical testing.

^3 Model based estimates based on a mixed model for repeated measures including treatment as a factor and baseline values as a covariate.

^4 Baseline value is the geometric mean.

Table 13. Mean Changes in Anthropometry and Cardiometabolic Parameters at Week 68 in Study 6 in East-Asian Patients with WEGOVY Injection

 | Study 6 (BMI ≥35 kg/m^2 with at least one comorbidity or BMI 27; to 34.9 kg/m^2 with at least two comorbidities)
Intention-to-treat | PLACEBO; N=101 | WEGOVY 1.7 mg; Injection; N=101 | WEGOVY 2.4 mg; Injection; N=199
Waist circumference (cm); Baseline; Change from baseline (LSMean^1); Difference from placebo (LSMean) | 103.8; -1.8 | 101.4; -7.7; -5.9 | 103.8; -11; -9.3
Systolic blood pressure (mmHg)^2; Baseline; Change from baseline (LSMean^1); Difference from placebo (LSMean) | 133; -5.3 | 135; -10.8; -5.4 | 133; -10.8; -5.5
Diastolic blood pressure (mmHg)^2; Baseline; Change from baseline (LSMean^1); Difference from placebo (LSMean) | 86; -2.2 | 85; -4.6; -2.4 | 83; -5.3; -3.1
Heart Rate^(2, 3); Baseline; Change from baseline (LSMean^1); Difference from placebo (LSMean) | 73; 2.4 | 73; 4.4; 2 | 73; 6.3; 3.9
HbA1c (%)^2; Baseline; Change from baseline (LSMean^1); Difference from placebo (LSMean) | 6.4; 0 | 6.4; -0.9; -0.9 | 6.4; -0.9; -0.9
Total Cholesterol (mg/dL)^2,4; Baseline; Percent change from baseline (LSMean^1); Relative difference from placebo (LSMean) | 203.1; 0.8 | 203.3; -6.6; -7.3 | 197.2; -8.7; -9.4
LDL Cholesterol (mg/dL)^2,4; Baseline; Percent change from baseline (LSMean^1); Relative difference from placebo (LSMean) | 123.3; -3.8 | 120.1; -10.1; -6.5 | 116.5; -14.6; -11.2
HDL Cholesterol (mg/dL)^2,4; Baseline; Percent change from baseline (LSMean^1); Relative difference from placebo (LSMean) | 48.7; 5.9 | 50.2; 6.7; 0.7 | 50.8; 9.2; 3.1
Triglyceride (mg/dL)^2,4; Baseline; Percent change from baseline (LSMean^1); Relative difference from placebo (LSMean) | 134.2; 5.5 | 138.8; -19.5; -23.7 | 127.1; -21.2; -25.3

Missing data were imputed from retrieved subjects of the same randomized treatment arm (RD-MI). At baseline, 24.7% of patients had type 2 diabetes mellitus.

^1 Model based estimates based on an analysis of covariance model including treatment and type 2 diabetes status as factors and baseline value as a covariate.

^2 Not included in the pre-specified hierarchical testing.

^3 Model based estimates based on a mixed model for repeated measures including treatment and type 2 diabetes status as factors and baseline values as a covariate.

^4 Baseline value is the geometric mean.

Table 14. Mean Changes in Anthropometry and Cardiometabolic Parameters in Study 7 with WEGOVY Tablet (Obesity or Overweight with Comorbidity)

 | Study 7 (Obesity or overweight with comorbidity)
Intention-to-treat | PLACEBO; N=102 | WEGOVY tablets 25 mg; N=205
Waist circumference (cm)^2; Baseline; Change from baseline (LSMean^1); Difference from placebo (LSMean) | 113.6; -2.8 | 114; -12.2; -9.4
Systolic blood pressure (mmHg)^2; Baseline; Change from baseline (LSMean^1); Difference from placebo (LSMean) | 131; -5.4 | 131; -7.0; -1.6
Diastolic blood pressure (mmHg)^2; Baseline; Change from baseline (LSMean^1); Difference from placebo (LSMean) | 83; -1.8 | 83; -2.8; -1.0
Heart Rate^2; Baseline; Change from baseline (LSMean^1); Difference from placebo (LSMean) | 74; 2.4 | 72; 2.7; 0.4
HbA1c (%)^2; Baseline; Change from baseline (LSMean^1); Difference from placebo (LSMean) | 5.7; -0.1 | 5.7; -0.3; -0.2
Total Cholesterol (mg/dL)^2,3; Baseline; Percent change from baseline (LSMean^1); Relative difference from placebo (LSMean) | 190.5; -2.2 | 191.4; -3.3; -1.2
LDL Cholesterol (mg/dL)^2,3; Baseline; Percent change from baseline (LSMean^1); Relative difference from placebo (LSMean) | 114.2; 0.2 | 111.1; -2.9; -3.1
HDL Cholesterol (mg/dL)^2,3; Baseline; Percent change from baseline (LSMean^1); Relative difference from placebo (LSMean) | 50.1; -1.1 | 49.6; 3.3; 4.5
Triglyceride (mg/dL)^2,3; Baseline; Percent change from baseline (LSMean^1); Relative difference from placebo (LSMean) | 117.5; -9.1 | 115.9; -18.1; -9.9

^1 Model based estimates are based on an analysis of covariance including treatment as a factor and baseline value as a covariate. Missing data were multiple imputed from retrieved subjects of the same randomized treatment arm (RD-MI). The imputation model was a linear regression of the endpoint with gender as factor and baseline value of the endpoint, timing and the value of last available observation – on study (LAO-OS) of the endpoint as covariates, imputed by treatment status.

RD-MI: Retrieved Drop-outs Multiple Imputation

^2 Not included in the pre-specified hierarchical testing.

^3 Baseline value is the geometric mean.

14.3 Weight Reduction and Long-term Maintenance Study of WEGOVY Injection in Pediatric Patients Aged 12 Years and Older with Obesity

Overview of Clinical Trial in Pediatric Patients

WEGOVY injection was evaluated to reduce excess body weight in pediatric patients aged 12 years of age and older with obesity in a 68-week, double-blind, randomized, parallel group, placebo-controlled, multi-center trial in 201 pubertal pediatric patients aged 12 years and older with BMI corresponding to ≥95th percentile standardized for age and sex (Study 8) (NCT#04102189). After a 12-week lifestyle run-in period (including dietary recommendations and physical activity counseling), patients were randomized 2:1 to WEGOVY injection once weekly or placebo once weekly. WEGOVY injection or matching placebo was escalated to 2.4 mg or maximally tolerated dose during a 16-week period followed by 52 weeks on maintenance dose. Of WEGOVY injection-treated patients who completed the trial, 86.7% were on the 2.4 mg dosage at the end of the trial; for 5% of patients, 1.7 mg was the maximum tolerated dosage.

The mean age was 15 years; 38% of patients were male; 79% were White, 8% were Black or African American, 2% were Asian, and 11% were of other or unknown race; and 11% were of Hispanic or Latino ethnicity. The mean baseline body weight was 108 kg, and mean BMI was 37 kg/m^2.

Results

The proportions of patients who discontinued study drug were 10% for the WEGOVY injection-treated group and 10% for the placebo-treated group.

The primary endpoint was percent change in BMI from baseline to Week 68. After 68 weeks, treatment with WEGOVY injection resulted in a statistically significant reduction in percent BMI compared with placebo. Greater proportions of patients treated with WEGOVY injection achieved ≥5% reduction in baseline BMI than those treated with placebo as shown in Table 15.

Table 15. Changes in Weight and BMI at Week 68 in Pediatric Patients with Obesity Aged 12 Years and Older in Study 8 with WEGOVY Injection

Intention-to-Treata | PLACEBO N=67 | WEGOVY Injection N=134
BMI
Baseline mean (kg/m^2) | 35.7 | 37.7
% change from baseline in BMI (LSMean) | 0.6 | -16.1
% difference from placebo (LSMean) (95% CI) |  | -16.7; (-20.3; -13.2)*
% of Patients with greater than or equal to 5% reduction in baseline BMIb | 19.7 | 77.1
% difference from placebo (LSMean) |  | 57.4
% of Patients with greater than or equal to 10% reduction in baseline BMIb | 7.7 | 65.1
% difference from placebo (LSMean) |  | 57.5
% of Patients with greater than or equal to 15% reduction in baseline BMIb | 4 | 57.8
% difference from placebo (LSMean) |  | 53.9
Body Weightb
Baseline mean (kg) | 102.6 | 109.9
% change from baseline (LSMean)a | 2.7 | -14.7
% difference from placebo (LSMean) |  | -17.4

LSMean = least squares mean; CI = confidence interval

a The intention-to-treat population includes all randomized patients. Missing data were imputed using available data according to value and timing of last available observation on treatment and endpoint’s baseline value from retrieved subjects (RD-MI). At week 68, the BMI was missing for 2.2% and 7.5% of patients randomized to WEGOVY injection and placebo, respectively.

b Parameters not included in the pre-specified hierarchical testing.

* p<0.0001 (unadjusted 2-sided) for superiority.

The time course of change in BMI with WEGOVY injection and placebo from baseline through Week 68 is depicted in Figure 9. The cumulative frequency distribution of change in BMI is shown in Figure 10.

Figure 9. Change from Baseline (%) in BMI in Pediatric Patients with Obesity Aged 12 Years and Older in Study 8 with WEGOVY Injection

Observed values for patients completing each scheduled visit, and estimates with multiple imputations from retrieved dropouts (RD-MI).

Figure 10. Change in BMI (%) from Baseline to Week 68 in Pediatric Patients with Obesity Aged 12 Years and Older in Study 8 with WEGOVY Injection

Observed data from in-trial period including imputed data for missing observations (RD-MI).

Effect of WEGOVY Injection on Anthropometry and Cardiometabolic Parameters in Pediatric Patients with Obesity Aged 12 Years and Older

Changes in waist circumference and cardiometabolic parameters with WEGOVY injection are shown in Table 16 for the study in pediatric patients aged 12 years and older.

Table 16. Mean Changes in Anthropometry and Cardiometabolic Parameters in Pediatric Patients with Obesity Aged 12 Years and Older in Study 8 with WEGOVY Injection

 | PLACEBO; N=67 |  | WEGOVY Injection; N=134
 | Baseline | Change from; Baseline; (LSMean) | Baseline | Change from; Baseline; (LSMean) | Difference; from placebo; (LSMean)
Waist Circumference (cm)^2 | 107.3 | -0.6 | 111.9 | -12.7 | -12.1
Systolic Blood Pressure (mmHg)^2 | 120 | -0.8 | 120 | -2.7 | -1.9
Diastolic Blood Pressure (mmHg)^2 | 73 | -0.8 | 73 | -1.4 | -0.6
Heart Rate^3 | 76 | -2.3 | 79 | 1.2 | 3.5
HbA1c (%)^2,4 | 5.4 | -0.1 | 5.5 | -0.4 | -0.2
 | Baseline | % Change; from Baseline; (LSMean) | Baseline | % Change; from Baseline; (LSMean) | Relative; difference from; placebo; (LSMean)
Total Cholesterol (mg/dL)^2,5 | 160.1 | -1.3 | 159.4 | -8.3 | -7.1
LDL Cholesterol (mg/dL)^2,5 | 91.7 | -3.6 | 89.8 | -9.9 | -6.6
HDL Cholesterol (mg/dL)^2,5 | 43.3 | 3.2 | 43.7 | 8 | 4.7
Triglycerides (mg/dL)^2,5 | 108 | 2.6 | 111.3 | -28.4 | -30.2

^1 Parameters listed in the table were not included in the pre-specified hierarchical testing.

^2 Missing data were imputed using available data according to value and timing of last available observation on treatment and endpoint’s baseline value from retrieved subjects (RD-MI). Model based estimates based on an analysis of covariance model including treatment and stratification groups (gender, Tanner stage group) and the interaction between stratification groups as factors and baseline value as a covariate.

^3 Model based estimates based on a mixed model for repeated measures including treatment as a factor and baseline value as a covariate all nested within visit.

^4 For patients without type 2 diabetes at randomization (N=129 for WEGOVY injection-treated patients and N=64 for placebo-treated patients).

^5 Baseline value is the geometric mean.

14.4 Noncirrhotic Metabolic Dysfunction-associated Steatohepatitis with Moderate to Advanced Liver Fibrosis in Adults Treated with WEGOVY Injection

Overview of Clinical Trial

The efficacy of WEGOVY injection was evaluated based on an efficacy analysis at Week 72 in Study 9 (NCT#04822181), a 240-week, randomized, double-blind, placebo-controlled trial. Enrolled patients had a baseline or recent liver biopsy showing clinically significant MASLD (metabolic dysfunction-associated steatotic liver disease), defined as MASH with fibrosis stage 2 or 3 and a non-alcoholic fatty liver disease (NAFLD) Activity Score (NAS) ≥4 with a score of 1 or more in steatosis, lobular inflammation, and hepatocyte ballooning. Efficacy determination was based on the effect of WEGOVY injection on resolution of steatohepatitis without worsening of liver fibrosis and on at least one stage improvement in liver fibrosis without worsening of steatohepatitis, on post-baseline liver biopsies collected at 72 weeks.

The Week 72 analysis included 800 F2 and F3 (at eligibility) patients randomized 1:2 to receive placebo (n=266) or WEGOVY once weekly (n=534), in addition to standard of care for cardiometabolic comorbidities and healthy lifestyle counseling. WEGOVY injection or matching placebo was escalated to 2.4 mg once weekly during the initial 16 weeks of the treatment period. Dose escalation could be prolonged or patients could remain at a lower dose if 2.4 mg once weekly was not tolerable.

Demographic and baseline characteristics were balanced between treatment and placebo groups. Overall, the median (Q1 to Q3) age of patients at baseline was 57 (49 to 65) years, 57% were female, 18% were Hispanic, 68% were White, 27% were Asian, and 0.6% were Black or African American. Median (Q1 to Q3) body mass index (BMI) was 34 (30 to 38) kg/m^2 and median (Q1 to Q3) body weight was 93 (79 to 110) kg. Baseline characteristics are presented in Table 17.

Table 17. Baseline Characteristics in Adults Patients with Noncirrhotic MASH with Stage 2 to Stage 3 Fibrosis in Study 9

Characteristic | Overall (N=800)
Fibrosis stage, n (%); F2; F3 | 250 (31); 550 (69)
Body Mass Index (BMI, kg/m^2), n (%)a; <25; 25-30; 30-35; ≥35 | 53 (7); 164 (21); 252 (32); 330 (41)
Lean MASH, n (%)b | 22 (3)
Type 2 Diabetes, n (%) | 447 (56)
Hypertension, n (%) | 503 (63)
Dyslipidemia, n (%) | 198 (25)
Statin use, n (%) | 300 (38)
Fibrosis Index Based on 4 Factors (FIB-4), Median (Q1, Q3)a | 1.6 (1.1, 2.3)
Enhanced Liver Fibrosis (ELF), Median (Q1, Q3) | 9.9 (9.3, 10.5)

a Less than 5% missingness in the variable is omitted.

b Lean MASH defined as BMI <25 kg/m^2 for non-Asian patients and BMI <23 kg/m^2 for Asian patients.

Among the 79% of the patients with vibration-controlled transient elastography (VCTE) at baseline, median (Q1 to Q3) VCTE was 10.9 (8.6 to 15.5) kPa, which may not be representative of the entire study population. The 21% of patients with missing VCTE at baseline had higher percentages of being female and having baseline diabetes, hypertension, and dyslipidemia.

Results

Table 18 presents the Week 72 histopathology primary endpoint results comparing WEGOVY injection with placebo on

1) the estimated percentage of patients with resolution of steatohepatitis and no worsening of liver fibrosis and
2) the estimated percentage of patients with at least one stage improvement in liver fibrosis and no worsening of steatohepatitis. The secondary endpoint results of the estimated percentage of patients with resolution of steatohepatitis and improvement in liver fibrosis at Week 72 are also presented. Two pathologists independently read the liver biopsies for each patient; a third pathologist performed adjudication if consensus could not be reached between the two pathologists. WEGOVY injection demonstrated improvement on these histopathology endpoints at Week 72 compared to placebo.

Table 18. Efficacy Results at Week 72 in Adult Patients with Noncirrhotic MASH with Stage 2 or

Stage 3 Fibrosis in Study 9 of WEGOVY Injection

 | Placebo; N=266 | WEGOVY Injection; N=534
Resolution of steatohepatitis and no worsening of liver fibrosis
Response Rate (%) | 34 | 63
Difference in response rate vs. placebo (95% CI) |  | 29 (21, 36)*
Improvement in liver fibrosis and no worsening of steatohepatitis
Response Rate (%) | 22 | 37
Difference in response rate vs. placebo (95% CI) |  | 14 (8, 21)*
Resolution of steatohepatitis and improvement in liver fibrosis
Response Rate (%) | 16 | 33
Difference in response rate vs. placebo (95% CI) |  | 17 (10, 23)*

* Results were statistically significant.

Endpoints were evaluated according to the MASH Clinical Research Network (CRN). Resolution of steatohepatitis is defined as a score of 0 to 1 for lobular inflammation, 0 for ballooning, and any value for steatosis. No worsening of steatohepatitis is defined as no increase from baseline in score for ballooning, lobular inflammation, or steatosis.

Estimated using pooled Mantel-Haenszel (MH) estimates stratified by baseline type 2 diabetes status (presence or absence) and baseline fibrosis stage (F2 or F3) with missing data handled by reference-based multiple imputation and 95% confidence intervals (CIs) calculated using Rubin’s rule to pool Sato’s estimate of standard errors across the imputed datasets.

Another secondary endpoint was the percent change in body weight from baseline to Week 72. Patients treated with WEGOVY injection (mean baseline body weight 95.4 kg) achieved an average of 10.5% weight loss from baseline at Week 72, and patients treated with placebo (mean baseline weight 97.6 kg) achieved an average of 2% weight loss from baseline at Week 72; treatment with WEGOVY injection resulted in an average of 8.5% greater weight loss from baseline compared to placebo (95% CI: 7.4% to 9.5%).

Starting at Week 12 and through Week 72, there was a trend of greater reductions from baseline in average ALT and AST in the WEGOVY injection group as compared to the placebo group.

16 HOW SUPPLIED/STORAGE AND HANDLING

WEGOVY Injection

How Supplied

WEGOVY injection is a clear, colorless solution in a prefilled, disposable, single-dose pen-injector with an integrated needle. It is supplied in cartons containing 4 pen-injectors in the following packaging configurations:

Total Strength per Total Volume | NDC
0.25 mg/0.5 mL | 0169-4525-14
0.5 mg/0.5 mL | 0169-4505-14
1 mg/0.5 mL | 0169-4501-14
1.7 mg/0.75 mL | 0169-4517-14
2.4 mg/0.75 mL | 0169-4524-14

Recommended Storage

Store the WEGOVY single-dose pen in the refrigerator from 2°C to 8°C (36°F to 46°F). If needed, prior to cap removal, the pen can be kept from 8°C to 30°C (46°F to 86°F) up to 28 days. Do not freeze. Protect WEGOVY from light. WEGOVY must be kept in the original carton until time of administration. Discard the WEGOVY pen after use.

WEGOVY Tablets

How Supplied

WEGOVY tablets are available as:

Tablet; strength | Description | Package; Configuration | NDC Number
1.5 mg | White to light yellow, round shaped debossed with “1.5” on one side and “novo” on the other side | Bottle of 30 tablets | 0169-4415-31
4 mg | White to light yellow, round shaped debossed with “4” on one side and “novo” on the other side | Bottle of 30 tablets | 0169-4404-31
9 mg | White to light yellow, round shaped debossed with “9” on one side and “novo” on the other side | Bottle of 30 tablets | 0169-4409-31
25 mg | White to light yellow, oval shaped debossed with “25” on one side and “novo” on the other side | Bottle of 30 tablets | 0169-4425-31

Recommended Storage

Store at 20°C to 25°C (68°F to 77°F); excursions permitted to 15°C to 30°C (59°F to 86°F) [see USP Controlled Room Temperature]. Store and dispense WEGOVY tablets in the original bottle. Store WEGOVY tablet in the original bottle until use to protect tablets from moisture. Store WEGOVY tablets in a dry place away from moisture.

17 PATIENT COUNSELING INFORMATION

Advise the patient to read the FDA-approved patient labeling (Medication Guide and Instructions for Use).

Risk of Thyroid C-cell Tumors

Inform patients that semaglutide causes thyroid C-cell tumors in rodents and that the human relevance of this finding has not been determined. Counsel patients to report symptoms of thyroid tumors (e.g., a lump in the neck, hoarseness, dysphagia, or dyspnea) to their physician [see Boxed Warning, Warnings and Precautions (5.1)].

Acute Pancreatitis

Inform patients of the potential risk for acute pancreatitis and its symptoms: severe abdominal pain that sometimes radiates to the back, and which may or may not be accompanied by nausea or vomiting. Instruct patients to discontinue WEGOVY promptly and contact their physician if pancreatitis is suspected [see Warnings and Precautions (5.2)].

Acute Gallbladder Disease

Inform patients of the risk of acute gallbladder disease. Advise patients that substantial or rapid weight loss can increase the risk of gallbladder disease, but that gallbladder disease may also occur in the absence of substantial or rapid weight loss. Instruct patients to contact their healthcare provider for appropriate clinical follow-up if gallbladder disease is suspected [see Warnings and Precautions (5.3)].

Hypoglycemia

Inform patients of the risk of hypoglycemia and educate patients on the signs and symptoms of hypoglycemia. Advise patients with diabetes mellitus on glycemic lowering therapy that they may have an increased risk of hypoglycemia when using WEGOVY and to report signs and/or symptoms of hypoglycemia to their healthcare provider [see Warnings and Precautions (5.4)].

Acute Kidney Injury Due to Volume Depletion

Inform patients of the potential risk of acute kidney injury due to dehydration associated with gastrointestinal adverse reactions. Advise patients to take precautions to avoid fluid depletion. Inform patients of the signs and symptoms of acute kidney injury and instruct them to promptly report any of these signs or symptoms or persistent (or extended) nausea, vomiting, and diarrhea to their healthcare provider [see Warnings and Precautions (5.5)].

Severe Gastrointestinal Adverse Reactions

Inform patients of the potential risk of severe gastrointestinal adverse reactions. Instruct patients to contact their healthcare provider if they have severe or persistent gastrointestinal symptoms [see Warnings and Precautions (5.6)].

Hypersensitivity Reactions

Inform patients that serious hypersensitivity reactions have been reported during postmarketing use of semaglutide, the active ingredient in WEGOVY. Advise patients on the symptoms of hypersensitivity reactions and instruct them to stop taking WEGOVY and seek medical advice promptly if such symptoms occur [see Warnings and Precautions (5.7)].

Diabetic Retinopathy Complications in Patients with Type 2 Diabetes

Inform patients with type 2 diabetes to contact their physician if changes in vision are experienced during treatment with WEGOVY [see Warnings and Precautions (5.8)].

Heart Rate Increase

Instruct patients to inform their healthcare providers of palpitations or feelings of a racing heartbeat while at rest during WEGOVY treatment [see Warnings and Precautions (5.9)].

Suicidal Behavior and Ideation

Advise patients to report emergence or worsening of depression, suicidal thoughts or behavior, and/or any unusual changes in mood or behavior. Inform patients that if they experience suicidal thoughts or behaviors, they should stop taking WEGOVY [see Warnings and Precautions (5.10)].

Pulmonary Aspiration During General Anesthesia or Deep Sedation

Inform patients that WEGOVY may cause their stomach to empty more slowly which may lead to complications with anesthesia or deep sedation during planned surgeries or procedures. Instruct patients to inform healthcare providers prior to any planned surgeries or procedures if they are taking WEGOVY [see Warnings and Precautions (5.11)].

Pregnancy

WEGOVY may cause fetal harm. Advise patients to inform their healthcare provider of a known or suspected pregnancy. Advise patients who are exposed to WEGOVY during pregnancy to contact Novo Nordisk at 1-877-390-2760 or www.wegovypregnancyregistry.com [see Use in Specific Populations (8.1)].

Missed Doses

Inform patients if a dose of WEGOVY injection is missed and the next scheduled dose is more than 2 days away (48 hours), administer WEGOVY injection as soon as possible. If one dose is missed and the next scheduled dose is less than 2 days away (48 hours), do not administer the dose. Inform patients to resume their regular once-weekly dosing schedule [see Dosage and Administration (2.4)].

Inform patients if a dose of WEGOVY tablets is missed, skip the missed dose and take the next dose the following day [see Dosage and Administration (2.4)].

Lactation

Advise females not to breastfeed during treatment with WEGOVY tablets [see Use in Specific Populations (8.2)].

Marketed by: Novo Nordisk Inc., Plainsboro, NJ 08536

For additional information about WEGOVY contact:

Novo Nordisk Inc.

800 Scudders Mill Road

Plainsboro, NJ 08536

1-833-934-6891

WEGOVY® is a registered trademark of Novo Nordisk A/S.

Patent Information: http://www.novonordisk-us.com/products/product-patents.html

© 2025 Novo Nordisk

Medication Guide

WEGOVY® (wee-GOH-vee)

(semaglutide)

injection, for subcutaneous use

WEGOVY® (wee-GOH-vee)

(semaglutide)

tablets, for oral use

Read this Medication Guide and Instructions for Use before you start using WEGOVY and each time you get a refill. There may be new information. This information does not take the place of talking to your healthcare provider about your medical condition or your treatment.

What is the most important information I should know about WEGOVY?

WEGOVY may cause serious side effects, including:

- Possible thyroid tumors, including cancer. Tell your healthcare provider if you get a lump or swelling in your neck, hoarseness, trouble swallowing, or shortness of breath. These may be symptoms of thyroid cancer. In studies with rodents, WEGOVY and other medicines that work like WEGOVY caused thyroid tumors, including thyroid cancer. It is not known if WEGOVY will cause thyroid tumors or a type of thyroid cancer called medullary thyroid carcinoma (MTC) in people.
- Do not use WEGOVY if you or any of your family have ever had a type of thyroid cancer called medullary thyroid carcinoma (MTC), or if you have an endocrine system condition called Multiple Endocrine Neoplasia syndrome type 2 (MEN 2).

What is WEGOVY?

- WEGOVY injection is a prescription medicine used with a reduced-calorie diet and increased physical activity to:
- reduce the risk of major cardiovascular events such as death, heart attack, or stroke in adults with known heart disease and with either obesity or overweight).
- help adults and children aged 12 years and older with obesity, or some adults with excess weight (overweight) who also have weight-related medical problems to lose weight and keep the weight off.
- treat adults with metabolic dysfunction-associated steatohepatitis (MASH) with moderate to advanced liver scarring (fibrosis), but not with cirrhosis of the liver.
- WEGOVY tablets are a prescription medicine used with a reduced-calorie diet and increased physical activity to:
  - reduce the risk of major cardiovascular events such as death, heart attack, or stroke in adults with known heart disease and with either obesity or overweight.
  - help adults with obesity, or some adults with excess weight (overweight) who also have weight-related medical problems to lose weight and keep the weight off.
- WEGOVY contains semaglutide and should not be used with other semaglutide-containing products or other GLP-1 receptor agonist medicines.
- It is not known if WEGOVY injection is safe and effective:
- to reduce the risk of major cardiovascular events (death, heart attack, or stroke) in people under 18 years.
- to help children under 12 years of age lose weight and keep the weight off.
- for the treatment of MASH in people under 18 years of age.
- It is not known if WEGOVY tablets are safe and effective for use in people under 18 years of age.

Do not use WEGOVY if:

- you or any of your family have ever had a type of thyroid cancer called MTC or if you have an endocrine system condition called MEN 2.
- you have had a serious allergic reaction to semaglutide or any of the ingredients in WEGOVY injection or WEGOVY tablets. See the end of this Medication Guide for a complete list of ingredients in WEGOVY injection and WEGOVY tablets. See “What are the possible side effects of WEGOVY?” for symptoms of a serious allergic reaction.

Before using WEGOVY, tell your healthcare provider if you have any other medical conditions, including if you:

- have or have had problems with your pancreas or kidneys.
- have type 2 diabetes and a history of diabetic retinopathy.
- have or have had depression or suicidal thoughts, or mental health issues.
- are scheduled to have surgery or other procedures that use anesthesia or deep sleepiness (deep sedation).
- are pregnant or plan to become pregnant. WEGOVY may harm your unborn baby. You should stop using WEGOVY 2 months before you plan to become pregnant.
- Pregnancy Exposure Registry: There is a pregnancy exposure registry for women who use WEGOVY during pregnancy. The purpose of this registry is to collect information about the health of you and your baby. Talk to your healthcare provider about how you can take part in this registry or you may contact Novo Nordisk at 1-877-390-2760 or www.wegovypregnancyregistry.com.
- are breastfeeding or plan to breastfeed. Breastfeeding is not recommended during treatment with WEGOVY tablets. It is not known if WEGOVY when received through an injection passes into your breast milk. You should talk with your healthcare provider about the best way to feed your baby while using WEGOVY.
Tell your healthcare provider about all the medicines you take, including prescription and over-the-counter medicines, vitamins, and herbal supplements. WEGOVY may affect the way some medicines work and some medicines may affect the way WEGOVY works. Tell your healthcare provider if you are taking other medicines to treat diabetes, including sulfonylureas or insulin. WEGOVY slows stomach emptying and can affect medicines that need to pass through the stomach quickly.

Know the medicines you take. Keep a list of them to show your healthcare provider and pharmacist when you get a new medicine.

How should I use WEGOVY?

- Use WEGOVY exactly as your healthcare provider tells you to.
- Use WEGOVY with a reduced-calorie diet and increased physical activity.
- If you take too much WEGOVY, you may have severe nausea, severe vomiting and severe low blood sugar. Call your healthcare provider or Poison Help line at 1-800-222-1222 or go to the nearest hospital emergency room right away. Advice is also available online at poisonhelp.org.

WEGOVY Injection

- Read the Instructions for Use that comes with WEGOVY.
- Your healthcare provider should show you how to use WEGOVY before you use it for the first time.
- WEGOVY is injected under the skin (subcutaneously) of your stomach (abdomen), thigh, or upper arm. Do not inject WEGOVY into a muscle (intramuscularly) or vein (intravenously).
- Change (rotate) your injection site with each injection. Do not use the same site for each injection.
- Use WEGOVY 1 time each week, on the same day each week, at any time of the day.
- If you need to change the day of the week, you may do so as long as your last dose of WEGOVY was given 2 or more days before.
- If you miss a dose of WEGOVY and the next scheduled dose is more than 2 days away (48 hours), take the missed dose as soon as possible. If you miss a dose of WEGOVY and the next schedule dose is less than 2 days away (48 hours), do not administer the dose. Take your next dose on the regularly scheduled day.
- If you miss doses of WEGOVY for 2 or more weeks, take your next dose on the regularly scheduled day or call your healthcare provider to talk about how to restart your treatment.
- You can take WEGOVY with or without food.

WEGOVY Tablets

- Take 1 WEGOVY tablet by mouth on an empty stomach in the morning with water (no more than 4 ounces). Do not take WEGOVY tablets with any other liquids besides water.
- Do not split, crush, chew or dissolve WEGOVY tablets. Swallow WEGOVY tablets whole.
- Do not take more than 1 WEGOVY tablet each day.
- After 30 minutes, you can eat, drink, or take other oral medicines.
- If you miss a dose of WEGOVY, skip the missed dose and go back to your regular schedule for the next dose.

What are the possible side effects of WEGOVY?

WEGOVY may cause serious side effects, including:

- See “What is the most important information I should know about WEGOVY?”
- inflammation of your pancreas (pancreatitis). Stop using WEGOVY and call your healthcare provider right away if you have severe pain in your stomach area (abdomen) that will not go away, with or without nausea or vomiting. Sometimes you may feel the pain from your abdomen to your back.
- gallbladder problems. WEGOVY may cause gallbladder problems including gallstones. Some gallbladder problems need surgery. Call your healthcare provider if you have any of the following symptoms:

- pain in your upper stomach (abdomen)

- yellowing of skin or eyes (jaundice)

- fever

- clay-colored stools

- increased risk of low blood sugar (hypoglycemia) in patients with type 2 diabetes, especially those who also take medicines to treat type 2 diabetes mellitus such as an insulin or a sulfonylureas. Low blood sugar in patients with type 2 diabetes who receive WEGOVY can be both a serious and common side effect. Talk to your healthcare provider about how to recognize and treat low blood sugar. You should check your blood sugar before you start taking WEGOVY and while you take WEGOVY. Signs and symptoms of low blood sugar may include:

- dizziness or light-headedness

- sweating

- shakiness

- blurred vision

- slurred speech

- weakness

- anxiety

- hunger

- headache

- irritability or mood changes

- confusion or drowsiness

- fast heartbeat

- feeling jittery

- dehydration leading to kidney problems. Diarrhea, nausea, and vomiting may cause a loss of fluids (dehydration) which may cause kidney problems. It is important for you to drink fluids to help reduce your chance of dehydration. Tell your healthcare provider right away if you have nausea, vomiting, or diarrhea that does not go away.
- severe stomach problems. Stomach problems, sometimes severe, have been reported in people who use WEGOVY. Tell your healthcare provider if you have stomach problems that are severe or will not go away.
- serious allergic reactions. Stop using WEGOVY and get medical help right away, if you have any symptoms of a serious allergic reaction including:

- swelling of your face, lips, tongue or throat

- severe rash or itching

- very rapid heartbeat

- problems breathing or swallowing

- fainting or feeling dizzy

- change in vision in people with type 2 diabetes. Tell your healthcare provider if you have changes in vision during treatment with WEGOVY.
- increased heart rate. WEGOVY can increase your heart rate while you are at rest. Your healthcare provider should check your heart rate while you take WEGOVY. Tell your healthcare provider if you feel your heart racing or pounding in your chest and it lasts for several minutes.
- depression or thoughts of suicide. You should pay attention to any mental changes, especially sudden changes in your mood, behaviors, thoughts, or feelings. Call your healthcare provider right away if you have any mental changes that are new, worse, or worry you.
- food or liquid getting into the lungs during surgery or other procedures that use anesthesia or deep sleepiness (deep sedation). WEGOVY may increase the chance of food getting into your lungs during surgery or other procedures. Tell all your healthcare providers that you are taking WEGOVY before you are scheduled to have surgery or other procedures.
The most common side effects of WEGOVY in adults or children aged 12 years and older may include:

- nausea

- stomach (abdomen) pain

- dizziness

- gas

- diarrhea

- headache

- feeling bloated

- stomach flu

- vomiting

- tiredness (fatigue)

- belching

- heartburn

- constipation

- upset stomach

- low blood sugar in people with type 2 diabetes

- runny nose or sore throat

Talk to your healthcare provider about any side effect that bothers you or does not go away. These are not all the possible side effects of WEGOVY.

Call your doctor for medical advice about side effects. You may report side effects to FDA at 1‑800‑FDA‑1088.

How should I store WEGOVY?

WEGOVY Injection

- Store the WEGOVY pen in the refrigerator between 36°F to 46°F (2°C to 8°C).
- If needed, before removing the pen cap, WEGOVY can be stored from 46°F to 86°F (8°C to 30°C) in the original carton for up to 28 days.
- Keep WEGOVY in the original carton to protect it from light.
- Do not freeze.
- Throw away the pen if WEGOVY has been frozen, has been exposed to light or temperatures above 86°F (30°C), or has been out of the refrigerator for 28 days or longer.

WEGOVY Tablets

- Store WEGOVY tablets at room temperature between 68°F and 77°F (20°C to 25°C).
- Store tablets in the original closed WEGOVY bottle until you are ready to take one. Do not store in any other container.
- Store in a dry place away from moisture.

Keep WEGOVY and all medicines out of the reach of children.

General information about the safe and effective use of WEGOVY.

Medicines are sometimes prescribed for purposes other than those listed in a Medication Guide. Do not use WEGOVY for a condition for which it was not prescribed. Do not give WEGOVY to other people, even if they have the same condition that you have. It may harm them. You can ask your pharmacist or healthcare provider for information about WEGOVY that is written for health professionals.

What are the ingredients in WEGOVY?

Active Ingredient: semaglutide

Inactive Ingredients in WEGOVY injection: disodium phosphate dihydrate, 1.42 mg; sodium chloride, 8.25 mg; water for injection; and hydrochloric acid or sodium hydroxide may be added to adjust pH.

Inactive Ingredients in WEGOVY tablets: salcaprozate sodium (SNAC) and magnesium stearate

Marketed by: Novo Nordisk Inc., Plainsboro, NJ 08536

WEGOVY® is a registered trademark of Novo Nordisk A/S.

Patent Information: http://novonordisk-us.com/products/product-patents.html

© 2025 Novo Nordisk

For more information, go to startWegovy.com or call 1-833-Wegovy-1.

This Medication Guide has been approved by the U.S. Food and Drug Administration. Revised: 1/2026

Instructions for Use

WEGOVY®

(semaglutide) injection

WEGOVY comes in five strengths:

Before you use your WEGOVY pen for the first time, talk to your healthcare provider or your caregiver about how to prepare and inject WEGOVY correctly.

Important information

Read this Instructions for Use before you start using WEGOVY. This information does not replace talking to your healthcare provider about your medical condition or treatment.

- Your WEGOVY pen is for 1 time use only. The WEGOVY pen is for subcutaneous (under the skin) use only.
- The dose of WEGOVY is already set on your pen.
- The needle is covered by the needle cover and the needle will not be seen.
- Do not remove the pen cap until you are ready to inject.
- Do not touch or push on the needle cover. You could get a needle stick injury.
- Your WEGOVY injection will start when the needle cover is pressed firmly against your skin.
- Do not remove the pen from your skin before the yellow bar in the pen window has stopped moving. The medicine may appear on the skin or squirt from the needle and you may not get your full dose of WEGOVY if:
- the pen is removed too early or
- you have not pressed the pen firmly against the skin for the entire injection.
- If the yellow bar does not start moving or stops during the injection, contact your healthcare provider or Novo Nordisk at startWegovy.com or call Novo Nordisk Inc. at 1-833-934-6891.
- The needle cover will lock when the pen is removed from your skin. You cannot stop the injection and restart it later.
- People who are blind or have vision problems should not use the WEGOVY pen without help from a person trained to use the WEGOVY pen.

How do I store WEGOVY?

- Store the WEGOVY pen in the refrigerator between 36°F to 46°F (2°C to 8°C).
- If needed, before removing the pen cap, WEGOVY can be stored from 46°F to 86°F (8°C to 30°C) in the original carton for up to 28 days.
- Keep WEGOVY in the original carton to protect it from light.
- Do not freeze.
- Throw away the pen if WEGOVY has been frozen, has been exposed to light or temperatures above 86°F (30°C), or has been out of the refrigerator for 28 days or longer.

Keep WEGOVY and all medicines out of the reach of children.

How to use your WEGOVY pen

Do not use your WEGOVY pen without receiving training from your healthcare provider. Make sure that you or your caregiver know how to give an injection with the pen before you start your treatment.

Read and follow the instructions so that you use your WEGOVY pen correctly:

Preparation

Step 1. Prepare for your injection.

- Supplies you will need to give your WEGOVY injection:
- WEGOVY pen
- 1 alcohol swab or soap and water
- 1 gauze pad or cotton ball
- 1 sharps disposable container for used WEGOVY pens

- Wash your hands.
- Check your WEGOVY pen.
Do not use your WEGOVY pen if:
- The pen appears to have been used or any part of the pen appears broken, for example if it has been dropped.
- The WEGOVY medicine is not clear and colorless through the pen window.
- The expiration date (EXP) has passed.

Contact Novo Nordisk at 1-833-934-6891 if your WEGOVY pen fails any of these checks.

Step 2. Choose your injection site.

- Your healthcare provider can help you choose the injection site that is best for you
  - You may inject into your upper leg (front of the thighs), lower stomach (keep 2 inches away from your belly button) or upper arm.
- Do not inject into an area where the skin is tender, bruised, red, or hard. Avoid injecting into areas with scars or stretch marks.
- You may inject in the same body area each week, but make sure it is not in the same spot each time.

Clean the injection site with an alcohol swab or soap and water. Do not touch the injection site after cleaning. Allow the skin to dry before injecting.

Injection

Step 3. Remove pen cap.

- Pull the pen cap straight off your pen.

Step 4. Inject WEGOVY.

- Push the pen firmly against your skin and keep applying pressure until the yellow bar has stopped moving.
  If the yellow bar does not start moving, press the pen more firmly against your skin.
- You will hear 2 clicks during the injection.
- Click 1: the injection has started.
- Click 2: the injection is ongoing.
- If you have problems with the injection, refer to the “Troubleshooting” section.

Throw away pen

Step 5. Throw away (dispose of) pen.

Safely dispose of the WEGOVY pen right away after each use. See “How do I throw away (dispose of) WEGOVY pens?”

- What if blood appears after injection?
If blood appears at the injection site, press the site lightly with a gauze pad or cotton ball.

- If you have problems injecting, change to a more firm injection site, such as upper leg, or upper arm or consider standing up while injecting into the lower stomach.
- If medicine appears on the skin or squirts from the needle, make sure the next time you inject to keep applying pressure until the yellow bar has stopped moving. Then you can lift the pen slowly from your skin.

How do I throw away (dispose of) WEGOVY pens?

Put the used WEGOVY pen in an FDA-cleared sharps disposal container right away after use. Do not throw away (dispose of) the pen in your household trash.

If you do not have an FDA-cleared sharps disposal container, you may use a household container that is:

- made of a heavy-duty plastic,
- able to be closed with a tight-fitting, puncture-resistant lid, without sharps being able to come out,
- upright and stable during use,
- leak-resistant, and
- properly labeled to warn of hazardous waste inside the container.

When your sharps disposal container is almost full, you will need to follow your community guidelines for the right way to dispose of your sharps disposal container. There may be state or local laws about how you should throw away used needles and syringes. For more information about safe sharps disposal, and for specific sharps disposal in the state that you live in, go to the FDA’s website at http://www.fda.gov/safesharpsdisposal.

- Do not reuse the pen.
- Do not recycle the pen or sharps disposal container, or throw them into household trash.

Important: Keep your WEGOVY pen, sharps disposal container and all medicines out of the reach of children.

How do I care for my pen?

Protect your pen

- Do not drop your pen or knock it against hard surfaces.
- Do not expose your pen to any liquids.
- If you think that your pen may be damaged, do not try to fix it. Use a new one.
- Keep the pen cap on until you are ready to inject. Your pen will no longer be sterile if you store an unused pen without the cap, if you pull the pen cap off and put it on again, or if the pen cap is missing. This could lead to an infection.
If you have any questions about WEGOVY, go to startWegovy.com or call Novo Nordisk Inc. at 1-833-Wegovy-1

Marketed by:

Novo Nordisk Inc.

Plainsboro, NJ 08536

For information about WEGOVY, go to

startWegovy.com or contact:

Novo Nordisk Inc.

800 Scudders Mill Road

Plainsboro, NJ 08536

1-833-Wegovy-1

WEGOVY ® is a registered trademark of Novo Nordisk A/S.

Patent Information: http://novonordisk-us.com/products/product-patents.html

© 2025 Novo Nordisk

This Instructions for Use has been approved by the U.S. Food and Drug Administration. Revised: 11/2025

Package/Label Display Panel – 0.25 mg Injection

NDC 0169-4525-14 List 452514

0.25 mg

wegovy®

(semaglutide) injection

0.25 mg/0.5 mL

Use Wegovy 1 time a week

4 Single-Dose Prefilled Pens

Each pen delivers a single dose of 0.25 mg semaglutide

For subcutaneous use only

Single-Dose only

Rx only

Contains: 4 Wegovy pens, Product Literature.

Dispense the enclosed Medication Guide to each patient.

Package/Label Display Panel – 0.5 mg Injection

NDC 0169-4505-14 List 450514

0.5 mg

wegovy®

(semaglutide) injection

0.5 mg/0.5 mL

Use Wegovy 1 time a week

4 Single-Dose Prefilled Pens

Each pen delivers a single dose of 0.5 mg semaglutide

For subcutaneous use only

Single-Dose only

Rx only

Contains: 4 Wegovy pens, Product Literature.

Dispense the enclosed Medication Guide to each patient.

Package/Label Display Panel – 1 mg Injection

NDC 0169-4501-14 List 450114

1 mg

wegovy®

(semaglutide) injection

1 mg/0.5 mL

Use Wegovy 1 time a week

4 Single-Dose Prefilled Pens

Each pen delivers a single dose of 1 mg semaglutide

For subcutaneous use only

Single-Dose only

Rx only

Contains: 4 Wegovy pens, Product Literature.

Dispense the enclosed Medication Guide to each patient.

Package/Label Display Panel – 1.7 mg Injection

NDC 0169-4517-14 List 451714

1.7 mg

wegovy®

(semaglutide) injection

1.7 mg/0.75 mL

Use Wegovy 1 time a week

4 Single-Dose Prefilled Pens

Each pen delivers a single dose of 1.7 mg semaglutide

For subcutaneous use only

Single-Dose only

Rx only

Contains: 4 Wegovy pens, Product Literature.

Dispense the enclosed Medication Guide to each patient.

Package/Label Display Panel – 2.4 mg Injection

NDC 0169-4524-14 List 452414

2.4 mg

wegovy®

(semaglutide) injection

2.4 mg/0.75 mL

Use Wegovy 1 time a week

4 Single-Dose Prefilled Pens

Each pen delivers a single dose of 2.4 mg semaglutide

For subcutaneous use only

Single-Dose only

Rx only

Contains: 4 Wegovy pens, Product Literature.

Dispense the enclosed Medication Guide to each patient.

Package/Label Display Panel – 1.5 mg Tablets

NDC 0169-4415-31 LIST 441531
wegovy® 1.5 mg

(semaglutide) Tablets

1.5 mg

Rx only

DISPENSE WITH MEDICATION GUIDE

30 tablets

Package/Label Display Panel – 4 mg Tablets

NDC 0169-4404-31 LIST 440431
wegovy® 4 mg

(semaglutide) Tablets

4 mg

Rx only

DISPENSE WITH MEDICATION GUIDE

30 tablets

Package/Label Display Panel – 9 mg Tablets

NDC 0169-4409-31 LIST 440931
wegovy® 9 mg

(semaglutide) Tablets

9 mg

Rx only

DISPENSE WITH MEDICATION GUIDE

30 tablets

Package/Label Display Panel – 25 mg Tablets

NDC 0169-4425-31 LIST 442531
wegovy® 25 mg

(semaglutide) Tablets

25 mg

Rx only

DISPENSE WITH MEDICATION GUIDE

30 tablets